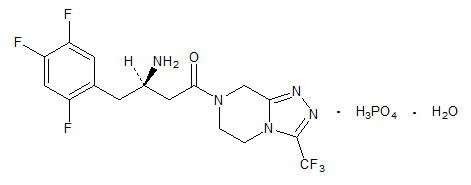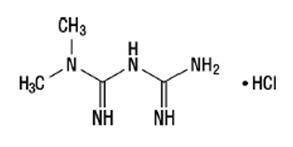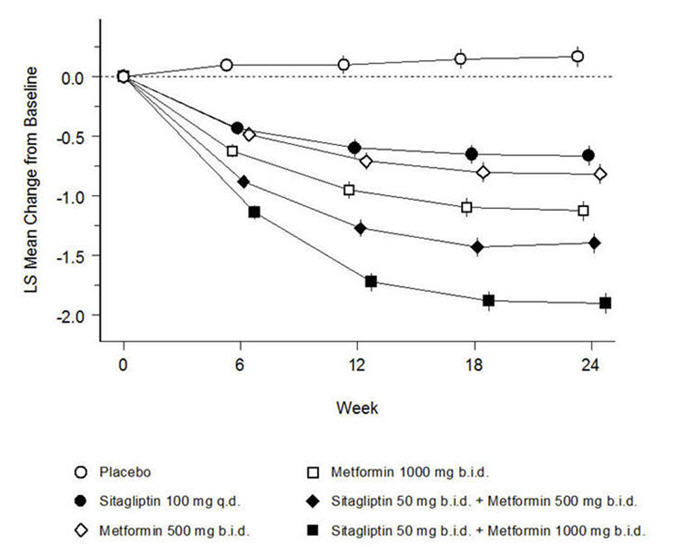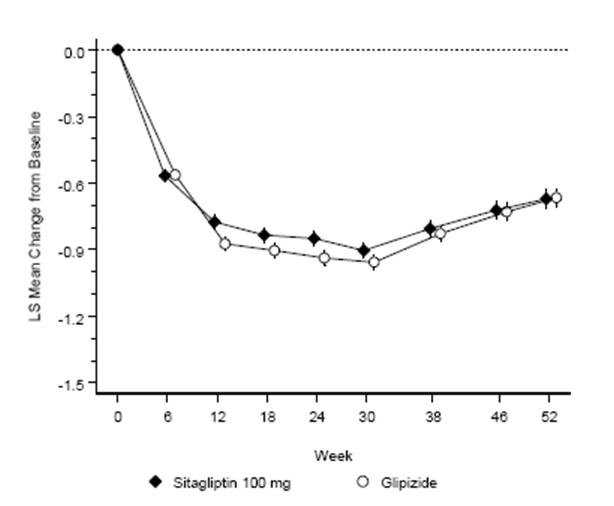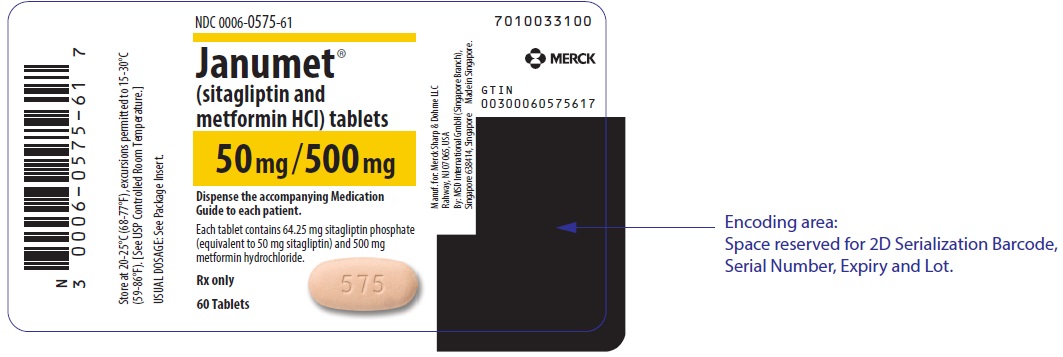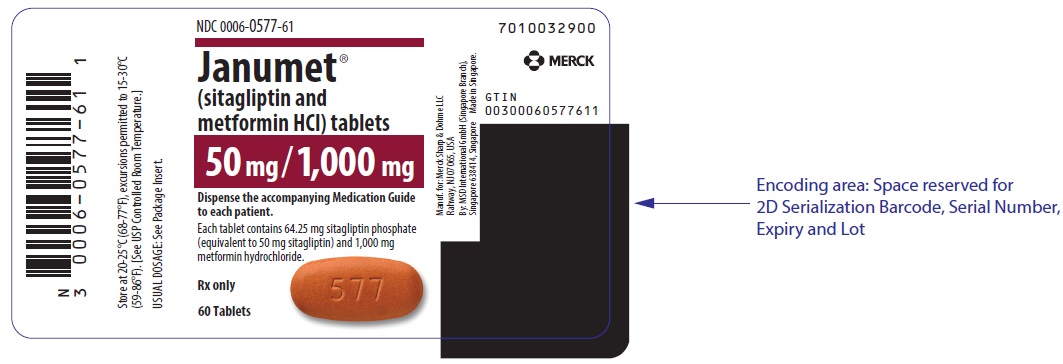 DRUG LABEL: JANUMET
NDC: 0006-0575 | Form: TABLET, FILM COATED
Manufacturer: Merck Sharp & Dohme LLC
Category: prescription | Type: HUMAN PRESCRIPTION DRUG LABEL
Date: 20250325

ACTIVE INGREDIENTS: SITAGLIPTIN PHOSPHATE 50 mg/1 1; METFORMIN HYDROCHLORIDE 500 mg/1 1
INACTIVE INGREDIENTS: FERROSOFERRIC OXIDE; MICROCRYSTALLINE CELLULOSE; POLYETHYLENE GLYCOL, UNSPECIFIED; POLYVINYL ALCOHOL, UNSPECIFIED; POVIDONE K30; FERRIC OXIDE RED; SODIUM LAURYL SULFATE; SODIUM STEARYL FUMARATE; TALC; TITANIUM DIOXIDE

HIGHLIGHTS OF PRESCRIBING INFORMATION

These highlights do not include all the information needed to use JANUMET safely and effectively. See full prescribing information for JANUMET.
JANUMET® (sitagliptin and metformin hydrochloride) tablets, for oral use
Initial U.S. Approval: 2007

WARNING: LACTIC ACIDOSIS

See full prescribing information for complete boxed warning.

- Postmarketing cases of metformin-associated lactic acidosis have resulted in death, hypothermia, hypotension, and resistant bradyarrhythmias. Symptoms included malaise, myalgias, respiratory distress, somnolence, and abdominal pain. Laboratory abnormalities included elevated blood lactate levels, anion gap acidosis, increased lactate/pyruvate ratio, and metformin plasma levels generally >5 mcg/mL. (5.1)
- Risk factors include renal impairment, concomitant use of certain drugs, age ≥65 years old, radiological studies with contrast, surgery and other procedures, hypoxic states, excessive alcohol intake, and hepatic impairment. Steps to reduce the risk of and manage metformin-associated lactic acidosis in these high-risk groups are provided in the Full Prescribing Information. (5.1)
- If lactic acidosis is suspected, discontinue JANUMET and institute general supportive measures in a hospital setting. Prompt hemodialysis is recommended. (5.1)

1 INDICATIONS AND USAGE

JANUMET is a combination of sitagliptin, a dipeptidyl peptidase-4 (DPP-4) inhibitor, and metformin hydrochloride (HCl), a biguanide, indicated as an adjunct to diet and exercise to improve glycemic control in adults with type 2 diabetes mellitus. (1)

Limitations of Use:

- JANUMET should not be used in patients with type 1 diabetes. (1)
- JANUMET has not been studied in patients with a history of pancreatitis. (1, 5.2)

2 DOSAGE AND ADMINISTRATION

- Take JANUMET orally twice daily with meals. (2.1)
- Individualize the dosage of JANUMET on the basis of the patient’s current regimen, effectiveness, and tolerability. (2.1)
- The maximum recommended daily dose is 100 mg of sitagliptin and 2000 mg of metformin HCl. (2.1)
- The recommended starting dose in patients not currently treated with metformin is 50 mg sitagliptin and 500 mg metformin HCl twice daily, with gradual dose escalation recommended to reduce gastrointestinal side effects associated with metformin. (2.1)
- The starting dose in patients already treated with metformin should provide sitagliptin dosed as 50 mg twice daily (100 mg total daily dose) and the dose of metformin already being taken. For patients taking metformin HCl 850 mg twice daily, the recommended starting dose of JANUMET is 50 mg sitagliptin and 1000 mg metformin HCl twice daily. (2.1)
- Prior to initiation, assess renal function with estimated glomerular filtration rate (eGFR) (2.2)
  - Do not use in patients with eGFR below 30 mL/min/1.73 m^2.
  - JANUMET is not recommended in patients with eGFR between 30 and less than 45 mL/min/1.73 m^2.
- JANUMET may need to be discontinued at time of, or prior to, iodinated contrast imaging procedures. (2.3)

3 DOSAGE FORMS AND STRENGTHS

JANUMET Tablets:

- sitagliptin 50 mg and metformin HCl 500 mg tablets
- sitagliptin 50 mg and metformin HCl 1000 mg tablets (3)

4 CONTRAINDICATIONS

- Severe renal impairment: (eGFR below 30 mL/min/1.73 m^2) (4)
- Metabolic acidosis, including diabetic ketoacidosis. (4)
- History of a serious hypersensitivity reaction to JANUMET, sitagliptin, or metformin, such as anaphylaxis or angioedema. (5.7, 6.2)

5 WARNINGS AND PRECAUTIONS

- Lactic Acidosis: See boxed warning. (5.1)
- Pancreatitis: There have been postmarketing reports of acute pancreatitis, including fatal and non-fatal hemorrhagic or necrotizing pancreatitis. If pancreatitis is suspected, promptly discontinue JANUMET. (5.2)
- Heart Failure: Has been observed with two other members of the DPP-4 inhibitor class. Consider risks and benefits of JANUMET in patients who have known risk factors for heart failure. Monitor patients for signs and symptoms. (5.3)
- Acute Renal Failure: Has been reported postmarketing, sometimes requiring dialysis. Before initiating JANUMET and at least annually thereafter, assess renal function. (5.4)
- Vitamin B12 Deficiency: Metformin may lower vitamin B12 levels. Measure hematologic parameters annually and vitamin B12 at 2 to 3 year intervals and manage any abnormalities. (5.5)
- Hypoglycemia with Concomitant Use with Insulin or Insulin Secretagogues: Increased risk of hypoglycemia when used in combination with insulin and/or an insulin secretagogue. A lower dose of insulin or insulin secretagogue may be required. (5.6)
- Hypersensitivity Reactions: There have been postmarketing reports of serious allergic and hypersensitivity reactions in patients treated with sitagliptin such as anaphylaxis, angioedema, and exfoliative skin conditions including Stevens-Johnson syndrome. Promptly stop JANUMET, assess for other potential causes, institute appropriate monitoring and treatment. (5.7)
- Severe and Disabling Arthralgia: Has been reported in patients taking DPP-4 inhibitors. Consider as a possible cause for severe joint pain and discontinue drug if appropriate. (5.8)
- Bullous Pemphigoid: There have been postmarketing reports requiring hospitalization in patients taking DPP-4 inhibitors. Tell patients to report development of blisters or erosions. If bullous pemphigoid is suspected, discontinue JANUMET. (5.9)

6 ADVERSE REACTIONS

- The most common adverse reactions reported in ≥5% of patients simultaneously started on sitagliptin and metformin and more commonly than in patients treated with placebo were diarrhea, upper respiratory tract infection, and headache. (6.1)

To report SUSPECTED ADVERSE REACTIONS, contact Merck Sharp & Dohme LLC at 1-877-888-4231 or FDA at 1-800-FDA-1088 or www.fda.gov/medwatch.

7 DRUG INTERACTIONS

- Carbonic anhydrase inhibitors may increase risk of lactic acidosis. Consider more frequent monitoring. (7)
- Drugs that reduce metformin clearance (such as ranolazine, vandetanib, dolutegravir, and cimetidine) may increase the accumulation of metformin. Consider the benefits and risks of concomitant use. (7)
- Alcohol can potentiate the effect of metformin on lactate metabolism. Warn patients against excessive alcohol intake. (7)

8 USE IN SPECIFIC POPULATIONS

- Females and Males of Reproductive Potential: Advise premenopausal females of the potential for an unintended pregnancy. (8.3)
- Geriatric Use: Assess renal function more frequently. (8.5)
- Hepatic Impairment: Avoid use in patients with hepatic impairment. (8.7)

FULL PRESCRIBING INFORMATION

WARNING: LACTIC ACIDOSIS

Postmarketing cases of metformin-associated lactic acidosis have resulted in death, hypothermia, hypotension, and resistant bradyarrhythmias. The onset of metformin-associated lactic acidosis is often subtle, accompanied only by nonspecific symptoms such as malaise, myalgias, respiratory distress, somnolence, and abdominal pain. Metformin-associated lactic acidosis was characterized by elevated blood lactate levels (>5 mmol/Liter), anion gap acidosis (without evidence of ketonuria or ketonemia), an increased lactate/pyruvate ratio, and metformin plasma levels generally >5 mcg/mL [see Warnings and Precautions (5.1)].

Risk factors for metformin-associated lactic acidosis include renal impairment, concomitant use of certain drugs (e.g., carbonic anhydrase inhibitors such as topiramate), age 65 years old or greater, having a radiological study with contrast, surgery and other procedures, hypoxic states (e.g., acute congestive heart failure), excessive alcohol intake, and hepatic impairment.

Steps to reduce the risk of and manage metformin-associated lactic acidosis in these high risk groups are provided in the full prescribing information [see Dosage and Administration (2.2), Contraindications (4), Warnings and Precautions (5.1), Drug Interactions (7), and Use in Specific Populations (8.6, 8.7)].

If metformin-associated lactic acidosis is suspected, immediately discontinue JANUMET and institute general supportive measures in a hospital setting. Prompt hemodialysis is recommended [see Warnings and Precautions (5.1)].

1 INDICATIONS AND USAGE

JANUMET is indicated as an adjunct to diet and exercise to improve glycemic control in adults with type 2 diabetes mellitus.

Limitations of Use

JANUMET should not be used in patients with type 1 diabetes mellitus.

JANUMET has not been studied in patients with a history of pancreatitis. It is unknown whether patients with a history of pancreatitis are at increased risk for the development of pancreatitis while using JANUMET. [See Warnings and Precautions (5.2).]

2 DOSAGE AND ADMINISTRATION

2.1 Recommended Dosing

- Take JANUMET orally twice daily with meals.
- Individualize the dosage of JANUMET on the basis of the patient’s current regimen, effectiveness, and tolerability.
- The maximum recommended daily dose is 100 mg of sitagliptin and 2000 mg of metformin hydrochloride (HCl).
- Do not split or divide JANUMET tablets.
- The recommended starting dose in patients not currently treated with metformin is 50 mg sitagliptin and 500 mg metformin HCl twice daily, with gradual dose escalation recommended to reduce gastrointestinal side effects associated with metformin.
- The starting dose in patients already treated with metformin should provide sitagliptin dosed as 50 mg twice daily (100 mg total daily dose) and the dose of metformin already being taken. For patients taking metformin HCl 850 mg twice daily, the recommended starting dose of JANUMET is 50 mg sitagliptin and 1000 mg metformin HCl twice daily.

2.2 Recommendations for Use in Renal Impairment

- Assess renal function prior to initiation of JANUMET and periodically thereafter.
- JANUMET is contraindicated in patients with an estimated glomerular filtration rate (eGFR) below 30 mL/min/1.73 m^2 [see Contraindications (4) and Warnings and Precautions (5.1)].
- JANUMET is not recommended in patients with an eGFR between 30 and less than 45 mL/min/1.73 m^2 because these patients require a lower dosage of sitagliptin than what is available in the fixed combination JANUMET product.

2.3 Discontinuation for Iodinated Contrast Imaging Procedures

Discontinue JANUMET at the time of, or prior to, an iodinated contrast imaging procedure in patients with an eGFR between 30 and 60 mL/min/1.73 m^2; in patients with a history of liver disease, alcoholism, or heart failure; or in patients who will be administered intra-arterial iodinated contrast. Re-evaluate eGFR 48 hours after the imaging procedure; restart JANUMET if renal function is stable [see Warnings and Precautions (5.1)].

3 DOSAGE FORMS AND STRENGTHS

Tablets:

- sitagliptin 50 mg and metformin HCl 500 mg tablets are light pink, capsule-shaped, film-coated tablets with “575” debossed on one side.
- sitagliptin 50 mg and metformin HCl 1000 mg tablets are red, capsule-shaped, film-coated tablets with “577” debossed on one side.

4 CONTRAINDICATIONS

JANUMET is contraindicated in patients with:

- Severe renal impairment (eGFR below 30 mL/min/1.73 m^2) [see Warnings and Precautions (5.1)].
- Acute or chronic metabolic acidosis, including diabetic ketoacidosis.
- History of a serious hypersensitivity reaction to JANUMET, sitagliptin, or metformin, such as anaphylaxis or angioedema. [See Warnings and Precautions (5.7); Adverse Reactions (6.2).]

5 WARNINGS AND PRECAUTIONS

5.1 Lactic Acidosis

There have been postmarketing cases of metformin-associated lactic acidosis, including fatal cases. These cases had a subtle onset and were accompanied by nonspecific symptoms such as malaise, myalgias, abdominal pain, respiratory distress, or increased somnolence; however, hypothermia, hypotension and resistant bradyarrhythmias have occurred with severe acidosis. Metformin-associated lactic acidosis was characterized by elevated blood lactate concentrations (>5 mmol/Liter), anion gap acidosis (without evidence of ketonuria or ketonemia), and an increased lactate/pyruvate ratio; metformin plasma levels were generally >5 mcg/mL. Metformin decreases liver uptake of lactate increasing lactate blood levels which may increase the risk of lactic acidosis, especially in patients at risk.

If metformin-associated lactic acidosis is suspected, general supportive measures should be instituted promptly in a hospital setting, along with immediate discontinuation of JANUMET. In JANUMET-treated patients with a diagnosis or strong suspicion of lactic acidosis, prompt hemodialysis is recommended to correct the acidosis and remove accumulated metformin (metformin HCl is dialyzable, with a clearance of up to 170 mL/min under good hemodynamic conditions). Hemodialysis has often resulted in reversal of symptoms and recovery.

Educate patients and their families about the symptoms of lactic acidosis and if these symptoms occur instruct them to discontinue JANUMET and report these symptoms to their health care provider.

For each of the known and possible risk factors for metformin-associated lactic acidosis, recommendations to reduce the risk of and manage metformin-associated lactic acidosis are provided below:

Renal Impairment

The postmarketing metformin-associated lactic acidosis cases primarily occurred in patients with significant renal impairment. The risk of metformin accumulation and metformin-associated lactic acidosis increases with the severity of renal impairment because metformin is substantially excreted by the kidney. Clinical recommendations based upon the patient's renal function include [see Dosage and Administration (2.2), Clinical Pharmacology (12.3)]:

- Before initiating JANUMET, obtain an estimated glomerular filtration rate (eGFR).
- JANUMET is contraindicated in patients with an eGFR below 30 mL/min/1.73 m^2 [see Contraindications (4)].
- JANUMET is not recommended in patients with an eGFR between 30 and less than 45 mL/min/1.73 m^2 because these patients require a lower dosage of sitagliptin than what is available in the fixed combination JANUMET product.
- Obtain an eGFR at least annually in all patients taking JANUMET. In patients at increased risk for the development of renal impairment (e.g., the elderly), renal function should be assessed more frequently.

Drug Interactions

The concomitant use of JANUMET with specific drugs may increase the risk of metformin-associated lactic acidosis: those that impair renal function, result in significant hemodynamic change, interfere with acid-base balance or increase metformin accumulation [see Drug Interactions (7)]. Therefore, consider more frequent monitoring of patients.

Age 65 or Greater

The risk of metformin-associated lactic acidosis increases with the patient's age because elderly patients have a greater likelihood of having hepatic, renal, or cardiac impairment than younger patients. Assess renal function more frequently in elderly patients [see Use in Specific Populations (8.5)].

Radiological Studies with Contrast

Administration of intravascular iodinated contrast agents in metformin-treated patients has led to an acute decrease in renal function and the occurrence of lactic acidosis. Stop JANUMET at the time of, or prior to, an iodinated contrast imaging procedure in patients with an eGFR between 30 and 60 mL/min/1.73 m^2; in patients with a history of hepatic impairment, alcoholism, or heart failure; or in patients who will be administered intra-arterial iodinated contrast. Re-evaluate eGFR 48 hours after the imaging procedure, and restart JANUMET if renal function is stable.

Surgery and Other Procedures

Withholding of food and fluids during surgical or other procedures may increase the risk for volume depletion, hypotension and renal impairment. JANUMET should be temporarily discontinued while patients have restricted food and fluid intake.

Hypoxic States

Several of the postmarketing cases of metformin-associated lactic acidosis occurred in the setting of acute congestive heart failure (particularly when accompanied by hypoperfusion and hypoxemia). Cardiovascular collapse (shock), acute myocardial infarction, sepsis, and other conditions associated with hypoxemia have been associated with lactic acidosis and may also cause prerenal azotemia. When such events occur, discontinue JANUMET.

Excessive Alcohol Intake

Alcohol potentiates the effect of metformin on lactate metabolism and this may increase the risk of metformin-associated lactic acidosis. Warn patients against excessive alcohol intake while receiving JANUMET.

Hepatic Impairment

Patients with hepatic impairment have developed with cases of metformin-associated lactic acidosis. This may be due to impaired lactate clearance resulting in higher lactate blood levels. Therefore, avoid use of JANUMET in patients with clinical or laboratory evidence of hepatic disease.

5.2 Pancreatitis

There have been postmarketing reports of acute pancreatitis, including fatal and non-fatal hemorrhagic or necrotizing pancreatitis, in patients taking JANUMET. After initiation of JANUMET, patients should be observed carefully for signs and symptoms of pancreatitis. If pancreatitis is suspected, JANUMET should promptly be discontinued and appropriate management should be initiated. It is unknown whether patients with a history of pancreatitis are at increased risk for the development of pancreatitis while using JANUMET.

5.3 Heart Failure

An association between dipeptidyl peptidase-4 (DPP-4) inhibitor treatment and heart failure has been observed in cardiovascular outcomes trials for two other members of the DPP-4 inhibitor class. These trials evaluated patients with type 2 diabetes mellitus and atherosclerotic cardiovascular disease.

Consider the risks and benefits of JANUMET prior to initiating treatment in patients at risk for heart failure, such as those with a prior history of heart failure and a history of renal impairment, and observe these patients for signs and symptoms of heart failure during therapy. Advise patients of the characteristic symptoms of heart failure and to immediately report such symptoms. If heart failure develops, evaluate and manage according to current standards of care and consider discontinuation of JANUMET.

5.4 Acute Renal Failure

There have been postmarketing reports of worsening renal function, including acute renal failure, sometimes requiring dialysis. Before initiation of therapy with JANUMET and at least annually thereafter, renal function should be assessed. In patients in whom development of renal dysfunction is anticipated, particularly in elderly patients, renal function should be assessed more frequently and JANUMET discontinued if evidence of renal impairment is present. JANUMET is contraindicated in patients with severe renal impairment [see Contraindications (4) and Warnings and Precautions (5.1)].

5.5 Vitamin B12 Deficiency

In controlled clinical trials of metformin of 29 weeks duration, a decrease to subnormal levels of previously normal serum vitamin B12 levels was observed in approximately 7% of patients. Such decrease, possibly due to interference with B12 absorption from the B12-intrinsic factor complex, may be associated with anemia but appears to be rapidly reversible with discontinuation of metformin or vitamin B12 supplementation. Certain individuals (those with inadequate vitamin B12 or calcium intake or absorption) appear to be predisposed to developing subnormal vitamin B12 levels. Measure hematologic parameters on an annual basis and vitamin B12 measurements at 2- to 3-year intervals in patients on JANUMET and manage any abnormalities [see Adverse Reactions (6.1)].

5.6 Hypoglycemia with Concomitant Use with Insulin or Insulin Secretagogues

JANUMET may increase the risk of hypoglycemia when combined with insulin and/or an insulin secretagogue (e.g., sulfonylurea) [see Adverse Reactions (6)]. A lower dose of insulin or insulin secretagogue may be required to minimize the risk of hypoglycemia when used in combination with JANUMET [see Drug Interactions (7)].

5.7 Hypersensitivity Reactions

There have been postmarketing reports of serious hypersensitivity reactions in patients treated with sitagliptin, one of the components of JANUMET. These reactions include anaphylaxis, angioedema, and exfoliative skin conditions including Stevens-Johnson syndrome. Onset of these reactions occurred within the first 3 months after initiation of treatment with sitagliptin, with some reports occurring after the first dose. If a hypersensitivity reaction is suspected, discontinue JANUMET, assess for other potential causes for the event, and institute alternative treatment for diabetes. [See Adverse Reactions (6.2).]

Angioedema has also been reported with other DPP-4 inhibitors. Use caution in a patient with a history of angioedema with another DPP-4 inhibitor because it is unknown whether such patients will be predisposed to angioedema with JANUMET.

5.8 Severe and Disabling Arthralgia

There have been postmarketing reports of severe and disabling arthralgia in patients taking DPP-4 inhibitors. The time to onset of symptoms following initiation of drug therapy varied from one day to years. Patients experienced relief of symptoms upon discontinuation of the medication. A subset of patients experienced a recurrence of symptoms when restarting the same drug or a different DPP-4 inhibitor. Consider DPP-4 inhibitors as a possible cause for severe joint pain and discontinue drug if appropriate.

5.9 Bullous Pemphigoid

Postmarketing cases of bullous pemphigoid requiring hospitalization have been reported with DPP-4 inhibitor use. In reported cases, patients typically recovered with topical or systemic immunosuppressive treatment and discontinuation of the DPP-4 inhibitor. Tell patients to report development of blisters or erosions while receiving JANUMET. If bullous pemphigoid is suspected, JANUMET should be discontinued and referral to a dermatologist should be considered for diagnosis and appropriate treatment.

6 ADVERSE REACTIONS

The following adverse reactions are also discussed elsewhere in the labeling:

- Lactic Acidosis [see Warnings and Precautions (5.1)]
- Pancreatitis [see Warnings and Precautions (5.2)]
- Heart Failure [see Warnings and Precautions (5.3)]
- Acute Renal Failure [see Warnings and Precautions (5.4)]
- Vitamin B12 Deficiency [see Warnings and Precautions (5.5)]
- Hypoglycemia with Concomitant Use with Insulin or Insulin Secretagogues [see Warnings and Precautions (5.6)]
- Hypersensitivity Reactions [see Warnings and Precautions (5.7)]
- Severe and Disabling Arthralgia [see Warnings and Precautions (5.8)]
- Bullous Pemphigoid [see Warnings and Precautions (5.9)]

6.1 Clinical Trials Experience

Because clinical trials are conducted under widely varying conditions, adverse reaction rates observed in the clinical trials of a drug cannot be directly compared to rates in the clinical trials of another drug and may not reflect the rates observed in practice.

Sitagliptin and Metformin Coadministration in Patients with Type 2 Diabetes Inadequately Controlled on Diet and Exercise

Table 1 summarizes the most common (≥5% of patients) adverse reactions reported (regardless of investigator assessment of causality) in a 24-week placebo-controlled factorial study in which sitagliptin and metformin were coadministered to patients with type 2 diabetes inadequately controlled on diet and exercise.

Table 1: Sitagliptin and Metformin Coadministered to Patients with Type 2 Diabetes Inadequately Controlled on Diet and Exercise: Adverse Reactions Reported (Regardless of Investigator Assessment of Causality) in ≥5% of Patients Receiving Combination Therapy (and Greater than in Patients Receiving Placebo) [Intent-to-treat population.]
 | Number of Patients (%)
 | Placebo | Sitagliptin 100 mg once daily | Metformin HCl 500 mg/ Metformin HCl 1000 mg twice daily [Data pooled for the patients given the lower and higher doses of metformin.] | Sitagliptin 50 mg twice daily + Metformin HCl 500 mg/ Metformin HCl 1000 mg twice daily
 | N = 176 | N = 179 | N = 364 | N = 372
Diarrhea | 7 (4.0) | 5 (2.8) | 28 (7.7) | 28 (7.5)
Upper Respiratory Tract Infection | 9 (5.1) | 8 (4.5) | 19 (5.2) | 23 (6.2)
Headache | 5 (2.8) | 2 (1.1) | 14 (3.8) | 22 (5.9)

Sitagliptin Add-on Therapy in Patients with Type 2 Diabetes Inadequately Controlled on Metformin Alone

In a 24-week placebo-controlled trial of sitagliptin 100 mg administered once daily added to a twice daily metformin regimen, there were no adverse reactions reported regardless of investigator assessment of causality in ≥5% of patients and more commonly than in patients given placebo. Discontinuation of therapy due to clinical adverse reactions was similar to the placebo treatment group (sitagliptin and metformin, 1.9%; placebo and metformin, 2.5%).

Gastrointestinal Adverse Reactions

The incidences of pre-selected gastrointestinal adverse experiences in patients treated with sitagliptin and metformin were similar to those reported for patients treated with metformin alone. See Table 2.

Table 2: Pre-selected Gastrointestinal Adverse Reactions (Regardless of Investigator Assessment of Causality) Reported in Patients with Type 2 Diabetes Receiving Sitagliptin and Metformin
 | Number of Patients (%)
 | Study of Sitagliptin and Metformin in Patients Inadequately Controlled on Diet and Exercise |  |  |  | Study of Sitagliptin Add-on in Patients Inadequately Controlled on Metformin Alone
 | Placebo | Sitagliptin 100 mg once daily | Metformin HCl 500 mg/ Metformin HCl 1000 mg twice daily [Data pooled for the patients given the lower and higher doses of metformin.] | Sitagliptin 50 mg twice daily + Metformin HCl 500 mg/ Metformin HCl 1000 mg twice daily | Placebo and Metformin HCl ≥1500 mg daily | Sitagliptin 100 mg once daily and Metformin HCl ≥1500 mg daily
 | N = 176 | N = 179 | N = 364 | N = 372 | N = 237 | N = 464
Diarrhea | 7 (4.0) | 5 (2.8) | 28 (7.7) | 28 (7.5) | 6 (2.5) | 11 (2.4)
Nausea | 2 (1.1) | 2 (1.1) | 20 (5.5) | 18 (4.8) | 2 (0.8) | 6 (1.3)
Vomiting | 1 (0.6) | 0 (0.0) | 2 (0.5) | 8 (2.2) | 2 (0.8) | 5 (1.1)
Abdominal Pain [Abdominal discomfort was included in the analysis of abdominal pain in the study of initial therapy.] | 4 (2.3) | 6 (3.4) | 14 (3.8) | 11 (3.0) | 9 (3.8) | 10 (2.2)

Sitagliptin in Combination with Metformin and Glimepiride

In a 24-week placebo-controlled study of sitagliptin 100 mg as add-on therapy in patients with type 2 diabetes inadequately controlled on metformin and glimepiride (sitagliptin, N=116; placebo, N=113), the adverse reactions reported regardless of investigator assessment of causality in ≥5% of patients treated with sitagliptin and more commonly than in patients treated with placebo were: hypoglycemia (Table 3) and headache (6.9%, 2.7%).

Sitagliptin in Combination with Metformin and Rosiglitazone

In a placebo-controlled study of sitagliptin 100 mg as add-on therapy in patients with type 2 diabetes inadequately controlled on metformin and rosiglitazone (sitagliptin, N=181; placebo, N=97), the adverse reactions reported regardless of investigator assessment of causality through Week 18 in ≥5% of patients treated with sitagliptin and more commonly than in patients treated with placebo were: upper respiratory tract infection (sitagliptin, 5.5%; placebo, 5.2%) and nasopharyngitis (6.1%, 4.1%). Through Week 54, the adverse reactions reported regardless of investigator assessment of causality in ≥5% of patients treated with sitagliptin and more commonly than in patients treated with placebo were: upper respiratory tract infection (sitagliptin, 15.5%; placebo, 6.2%), nasopharyngitis (11.0%, 9.3%), peripheral edema (8.3%, 5.2%), and headache (5.5%, 4.1%).

Sitagliptin in Combination with Metformin and Insulin

In a 24-week placebo-controlled study of sitagliptin 100 mg as add-on therapy in patients with type 2 diabetes inadequately controlled on metformin and insulin (sitagliptin, N=229; placebo, N=233), the only adverse reaction reported regardless of investigator assessment of causality in ≥5% of patients treated with sitagliptin and more commonly than in patients treated with placebo was hypoglycemia (Table 3).

Hypoglycemia

In the above studies (N=5), adverse reactions of hypoglycemia were based on all reports of symptomatic hypoglycemia; a concurrent glucose measurement was not required although most (77%) reports of hypoglycemia were accompanied by a blood glucose measurement ≤70 mg/dL. When the combination of sitagliptin and metformin was coadministered with a sulfonylurea or with insulin, the percentage of patients reporting at least one adverse reaction of hypoglycemia was higher than that observed with placebo and metformin coadministered with a sulfonylurea or with insulin (Table 3).

Table 3: Incidence and Rate of Hypoglycemia [Adverse reactions of hypoglycemia were based on all reports of symptomatic hypoglycemia; a concurrent glucose measurement was not required: Intent-to-treat population.] (Regardless of Investigator Assessment of Causality) in Placebo-Controlled Clinical Studies of Sitagliptin in Combination with Metformin Coadministered with Glimepiride or Insulin
Add-On to Glimepiride + Metformin (24 weeks) | Sitagliptin 100 mg + Metformin + Glimepiride | Placebo + Metformin + Glimepiride
 | N = 116 | N = 113
Overall (%) | 19 (16.4) | 1 (0.9)
Rate (episodes/patient-year) [Based on total number of events (i.e., a single patient may have had multiple events).] | 0.82 | 0.02
Severe (%) [Severe events of hypoglycemia were defined as those events requiring medical assistance or exhibiting depressed level/loss of consciousness or seizure.] | 0 (0.0) | 0 (0.0)
Add-On to Insulin + Metformin (24 weeks) | Sitagliptin 100 mg + Metformin + Insulin | Placebo + Metformin + Insulin
 | N = 229 | N = 233
Overall (%) | 35 (15.3) | 19 (8.2)
Rate (episodes/patient-year) | 0.98 | 0.61
Severe (%) | 1 (0.4) | 1 (0.4)

The overall incidence of reported adverse reactions of hypoglycemia in patients with type 2 diabetes inadequately controlled on diet and exercise was 0.6% in patients given placebo, 0.6% in patients given sitagliptin alone, 0.8% in patients given metformin alone, and 1.6% in patients given sitagliptin in combination with metformin. In patients with type 2 diabetes inadequately controlled on metformin alone, the overall incidence of adverse reactions of hypoglycemia was 1.3% in patients given add-on sitagliptin and 2.1% in patients given add-on placebo.

In the study of sitagliptin and add-on combination therapy with metformin and rosiglitazone, the overall incidence of hypoglycemia was 2.2% in patients given add-on sitagliptin and 0.0% in patients given add-on placebo through Week 18. Through Week 54, the overall incidence of hypoglycemia was 3.9% in patients given add-on sitagliptin and 1.0% in patients given add-on placebo.

In an additional, 30-week placebo-controlled, study of patients with type 2 diabetes inadequately controlled with metformin comparing the maintenance of sitagliptin 100 mg versus withdrawal of sitagliptin when initiating basal insulin therapy, the event rate and incidence of documented symptomatic hypoglycemia (blood glucose measurement ≤70 mg/dL) did not differ between the sitagliptin and placebo groups.

Vital Signs and Electrocardiograms

With the combination of sitagliptin and metformin, no clinically meaningful changes in vital signs or in ECG (including in QTc interval) were observed.

Pancreatitis

In a pooled analysis of 19 double-blind clinical trials that included data from 10,246 patients randomized to receive sitagliptin 100 mg/day (N=5429) or corresponding (active or placebo) control (N=4817), the incidence of acute pancreatitis was 0.1 per 100 patient-years in each group (4 patients with an event in 4708 patient-years for sitagliptin and 4 patients with an event in 3942 patient-years for control).

Sitagliptin

The most common adverse experience in sitagliptin monotherapy reported regardless of investigator assessment of causality in ≥5% of patients and more commonly than in patients given placebo was nasopharyngitis.

Metformin

The most common (>5%) established adverse reactions due to initiation of metformin therapy are diarrhea, nausea/vomiting, flatulence, abdominal discomfort, indigestion, asthenia, and headache.

Laboratory Tests

Sitagliptin

The incidence of laboratory adverse reactions was similar in patients treated with sitagliptin and metformin (7.6%) compared to patients treated with placebo and metformin (8.7%). In most but not all studies, a small increase in white blood cell count (approximately 200 cells/microL difference in WBC vs placebo; mean baseline WBC approximately 6600 cells/microL) was observed due to a small increase in neutrophils. This change in laboratory parameters is not considered to be clinically relevant.

Metformin

In controlled clinical trials of metformin of 29 weeks duration, a decrease to subnormal levels of previously normal serum vitamin B12 levels, without clinical manifestations, was observed in approximately 7% of patients. Such decrease, possibly due to interference with B12 absorption from the B12-intrinsic factor complex, is, however, very rarely associated with anemia and appears to be rapidly reversible with discontinuation of metformin or vitamin B12 supplementation.

6.2 Postmarketing Experience

Additional adverse reactions have been identified during postapproval use of JANUMET, sitagliptin, or metformin. Because these reactions are reported voluntarily from a population of uncertain size, it is generally not possible to reliably estimate their frequency or establish a causal relationship to drug exposure.

Hypersensitivity reactions including anaphylaxis, angioedema, rash, urticaria, cutaneous vasculitis, and exfoliative skin conditions including Stevens-Johnson syndrome; upper respiratory tract infection; hepatic enzyme elevations; acute pancreatitis, including fatal and non-fatal hemorrhagic and necrotizing pancreatitis [see Indications and Usage (1)]; worsening renal function, including acute renal failure (sometimes requiring dialysis) and tubulointerstitial nephritis; severe and disabling arthralgia; bullous pemphigoid; constipation; vomiting; headache; myalgia; pain in extremity; back pain; pruritus; mouth ulceration; stomatitis; cholestatic, hepatocellular, and mixed hepatocellular liver injury; rhabdomyolysis.

7 DRUG INTERACTIONS

Table 4 presents clinically significant drug interactions with JANUMET:

Table 4: Clinically Significant Drug Interactions with JANUMET
Carbonic Anhydrase Inhibitors
Clinical Impact: | Carbonic anhydrase inhibitors frequently cause a decrease in serum bicarbonate and induce non-anion gap, hyperchloremic metabolic acidosis. Concomitant use of these drugs with JANUMET may increase the risk for lactic acidosis.
Intervention: | Consider more frequent monitoring of these patients.
Examples: | Topiramate, zonisamide, acetazolamide or dichlorphenamide.
Drugs that Reduce Metformin Clearance
Clinical Impact: | Concomitant use of drugs that interfere with common renal tubular transport systems involved in the renal elimination of metformin (e.g., organic cationic transporter-2 [OCT2] / multidrug and toxin extrusion [MATE] inhibitors) could increase systemic exposure to metformin and may increase the risk for lactic acidosis [see Clinical Pharmacology (12.3)].
Intervention: | Consider the benefits and risks of concomitant use with JANUMET.
Examples: | Ranolazine, vandetanib, dolutegravir, and cimetidine.
Alcohol
Clinical Impact: | Alcohol is known to potentiate the effect of metformin on lactate metabolism.
Intervention: | Warn patients against alcohol intake while receiving JANUMET.
Insulin Secretagogues or Insulin
Clinical Impact: | Coadministration of JANUMET with an insulin secretagogue (e.g., sulfonylurea) or insulin may increase the risk of hypoglycemia.
Intervention: | Patients receiving an insulin secretagogue or insulin may require lower doses of the insulin secretagogue or insulin.
Drugs Affecting Glycemic Control
Clinical Impact: | Certain drugs tend to produce hyperglycemia and may lead to loss of glycemic control.
Intervention: | When such drugs are administered to a patient receiving JANUMET, observe the patient closely for loss of blood glucose control. When such drugs are withdrawn from a patient receiving JANUMET, observe the patient closely for hypoglycemia.
Examples: | Thiazides and other diuretics, corticosteroids, phenothiazines, thyroid products, estrogens, oral contraceptives, phenytoin, nicotinic acid, sympathomimetics, calcium channel blockers, and isoniazid.

8 USE IN SPECIFIC POPULATIONS

8.1 Pregnancy

Risk Summary

The limited available data with JANUMET in pregnant women are not sufficient to inform a drug-associated risk for major birth defects and miscarriage. Published studies with metformin use during pregnancy have not reported a clear association with metformin and major birth defect or miscarriage risk [see Data]. There are risks to the mother and fetus associated with poorly controlled diabetes in pregnancy [see Clinical Considerations]. No adverse developmental effects were observed when sitagliptin was administered to pregnant rats and rabbits during organogenesis at oral doses up to 30-times and 20-times, respectively, the 100 mg clinical dose, based on AUC. No adverse developmental effects were observed when metformin was administered to pregnant Sprague Dawley rats and rabbits during organogenesis at doses up to 2- and 6-times, respectively, a 2000 mg clinical dose, based on body surface area [see Data].

The estimated background risk of major birth defects is 6-10% in women with pre-gestational diabetes with a Hemoglobin A1c >7% and has been reported to be as high as 20-25% in women with a Hemoglobin A1c >10%. In the U.S. general population, the estimated background risk of major birth defects and miscarriage in clinically recognized pregnancies is 2-4% and 15-20% respectively.

Clinical Considerations

Disease-Associated Maternal and/or Embryo/Fetal Risk

Poorly controlled diabetes in pregnancy increases the maternal risk for diabetic ketoacidosis, pre-eclampsia, spontaneous abortions, preterm delivery, and delivery complications. Poorly controlled diabetes increases the fetal risk for major birth defects, still birth, and macrosomia related morbidity.

Data

Human Data

Published data from post-marketing studies do not report a clear association with metformin and major birth defects, miscarriage, or adverse maternal or fetal outcomes when metformin is used during pregnancy. However, these studies cannot definitely establish the absence of any risk because of methodological limitations, including small sample size and inconsistent comparator groups.

Animal Data

Sitagliptin and Metformin

No animal reproduction studies were conducted with the coadministration of sitagliptin and metformin.

Sitagliptin

In embryo-fetal development studies, sitagliptin administered to pregnant rats and rabbits during organogenesis (gestation day 6 to 20) did not adversely affect developmental outcomes at oral doses up to 250 mg/kg (30-times the 100 mg clinical dose) and 125 mg/kg (20-times the 100 mg clinical dose), respectively, based on AUC. Higher doses in rats associated with maternal toxicity increased the incidence of rib malformations in offspring at 1000 mg/kg, or approximately 100-times the clinical dose, based on AUC. Placental transfer of sitagliptin was observed in pregnant rats and rabbits.

Sitagliptin administered to female rats from gestation day 6 to lactation day 21 caused no functional or behavioral toxicity in offspring of rats at doses up to 1000 mg/kg.

Metformin

Metformin did not cause adverse developmental effects when administered to pregnant Sprague Dawley rats and rabbits up to 600 mg/kg/day during the period of organogenesis. This represents an exposure of about 2- and 6-times a 2000 mg clinical dose based on body surface area (mg/m^2) for rats and rabbits, respectively.

8.2 Lactation

Risk Summary

There is no information regarding the presence of JANUMET in human milk, the effects on the breastfed infant, or the effects on milk production. Limited published studies report that metformin is present in human milk [see Data]. There are no reports of adverse effects on breastfed infants exposed to metformin. There is no information on the effects of metformin on milk production. Sitagliptin is present in rat milk and therefore possibly present in human milk [see Data]. The developmental and health benefits of breastfeeding should be considered along with the mother's clinical need for JANUMET and any potential adverse effects on the breastfed infant from JANUMET or from the underlying maternal condition.

Data

Sitagliptin

Sitagliptin is secreted in the milk of lactating rats at a milk to plasma ratio of 4:1.

Metformin

Published clinical lactation studies report that metformin is present in human milk, which resulted in infant doses approximately 0.11% to 1% of the maternal weight-adjusted dosage and a milk/plasma ratio ranging between 0.13 and 1. However, the studies were not designed to definitely establish the risk of use of metformin during lactation because of small sample size and limited adverse event data collected in infants.

8.3 Females and Males of Reproductive Potential

Discuss the potential for unintended pregnancy with premenopausal women as therapy with metformin may result in ovulation in some anovulatory women.

8.4 Pediatric Use

The safety and effectiveness of JANUMET have not been established in pediatric patients.

Three 20-week double-blind, placebo-controlled studies each with 34-week extensions were conducted to evaluate the efficacy and safety of sitagliptin in 410 pediatric patients aged 10 to 17 years with inadequately controlled type 2 diabetes, with or without insulin therapy (HbA1c 6.5-10% for patients not on insulin, HbA1c 7-10% for patients on insulin). At study entry, patients in study 1 were not treated with oral antihyperglycemic agents; patients in studies 2 and 3 were on maximally tolerated metformin therapy. The primary efficacy endpoint was the change from baseline in HbA1c after 20 weeks of therapy. The pre-specified primary efficacy analyses included data from study 1 and pooled data from studies 2 and 3, regardless of glycemic rescue or treatment discontinuation.

In both efficacy analyses, the effect of treatment with sitagliptin was not significantly different from placebo. In study 1, the mean baseline HbA1c was 7.5%, and 12% of patients were on insulin therapy. At week 20, the change from baseline in HbA1c in patients treated with sitagliptin (N=95) was 0.06% compared to 0.23% in patients treated with placebo (N=95), a difference of -0.17% (95% CI: -0.62, 0.28). In studies 2 and 3, the mean baseline HbA1c was 8.0%, 15% of patients were on insulin and 72% were on metformin HCl doses of greater than 1,500 mg daily. At week 20, the change from baseline in HbA1c in patients treated with sitagliptin (N=107) was -0.23% compared to 0.09% in patients treated with placebo (N=113), a difference of -0.33% (95% CI: -0.70, 0.05).

8.5 Geriatric Use

JANUMET

In general, dose selection for an elderly patient should be cautious, usually starting at the low end of the dosing range, reflecting the greater frequency of decreased hepatic, renal, or cardiac function, and of concomitant disease or other drug therapy and the higher risk of lactic acidosis. Renal function should be assessed more frequently in elderly patients. [See Contraindications (4); Warnings and Precautions (5.1, 5.4); Clinical Pharmacology (12.3).]

Sitagliptin

Of the total number of subjects (N=3884) in clinical studies of sitagliptin, 725 patients were 65 years and over, while 61 patients were 75 years and over. No overall differences in safety or effectiveness were observed between subjects 65 years and over and younger subjects. While this and other reported clinical experience have not identified differences in responses between the elderly and younger patients, greater sensitivity of some older individuals cannot be ruled out.

Metformin

Controlled clinical studies of metformin did not include sufficient numbers of elderly patients to determine whether they respond differently from younger patients, although other reported clinical experience has not identified differences in responses between the elderly and young patients.

8.6 Renal Impairment

JANUMET

JANUMET is not recommended in patients with an eGFR between 30 and less than 45 mL/min/1.73 m^2 because these patients require a lower dosage of sitagliptin than what is available in the fixed dose combination JANUMET product. JANUMET is contraindicated in severe renal impairment, patients with an eGFR below 30 mL/min/1.73 m^2. [See Dosage and Administration (2.2), Contraindications (4), Warnings and Precautions (5.1) and Clinical Pharmacology (12.3).]

Sitagliptin

Sitagliptin is excreted by the kidney, and sitagliptin exposure is increased in patients with renal impairment. [See Clinical Pharmacology (12.3).]

Metformin

Metformin is substantially excreted by the kidney, and the risk of metformin accumulation and lactic acidosis increases with the degree of renal impairment.

8.7 Hepatic Impairment

Use of metformin in patients with hepatic impairment has been associated with some cases of lactic acidosis. JANUMET is not recommended in patients with hepatic impairment. [See Warnings and Precautions (5.1).]

10 OVERDOSAGE

In the event of overdose with JANUMET, contact the Poison Control Center.

In the event of an overdose, it is reasonable to employ supportive measures, e.g., remove unabsorbed material from the gastrointestinal tract, employ clinical monitoring (including obtaining an electrocardiogram), and institute supportive therapy as indicated by the patient's clinical status.

Sitagliptin is modestly dialyzable. In clinical studies, approximately 13.5% of the dose was removed over a 3- to 4-hour hemodialysis session. Prolonged hemodialysis may be considered if clinically appropriate. It is not known if sitagliptin is dialyzable by peritoneal dialysis.

Overdose of metformin has occurred, including ingestion of amounts greater than 50 grams. Hypoglycemia was reported in approximately 10% of cases, but no causal association with metformin has been established. Lactic acidosis has been reported in approximately 32% of metformin overdose cases [see Warnings and Precautions (5.1)]. Metformin is dialyzable with a clearance of up to 170 mL/min under good hemodynamic conditions. Therefore, hemodialysis may be useful for removal of accumulated drug from patients in whom metformin overdosage is suspected.

11 DESCRIPTION

JANUMET (sitagliptin and metformin HCl) tablets for oral use contain two antihyperglycemic drugs: sitagliptin and metformin HCl.

Sitagliptin

Sitagliptin is an orally-active inhibitor of the dipeptidyl peptidase-4 (DPP-4) enzyme. Sitagliptin is present in JANUMET tablets in the form of sitagliptin phosphate monohydrate. Sitagliptin phosphate monohydrate is described chemically as 7-[(3R)-3-amino-1-oxo-4-(2,4,5-trifluorophenyl)butyl]-5,6,7,8-tetrahydro-3-(trifluoromethyl)-1,2,4-triazolo[4,3-a]pyrazine phosphate (1:1) monohydrate with an empirical formula of C16H15F6N5O∙H3PO4∙H2O and a molecular weight of 523.32. The structural formula is:

Sitagliptin phosphate monohydrate is a white to off-white, crystalline, non-hygroscopic powder. It is soluble in water and N,N-dimethyl formamide; slightly soluble in methanol; very slightly soluble in ethanol, acetone, and acetonitrile; and insoluble in isopropanol and isopropyl acetate.

Metformin HCl

Metformin HCl (N,N-dimethylimidodicarbonimidic diamide hydrochloride) is not chemically or pharmacologically related to any other classes of oral antihyperglycemic agents. Metformin HCl is a white to off-white crystalline compound with a molecular formula of C4H11N5∙HCl and a molecular weight of 165.63. Metformin HCl is freely soluble in water and is practically insoluble in acetone, ether, and chloroform. The pKa of metformin HCl is 12.4. The pH of a 1% aqueous solution of metformin HCl is 6.68. The structural formula is as shown:

JANUMET

JANUMET is available as film-coated tablets containing:

- 64.25 mg sitagliptin monohydrate equivalent to 50 mg of sitagliptin and 389.93 mg of metformin equivalent to 500 mg metformin HCl (JANUMET 50/500).
- 64.25 mg sitagliptin monohydrate equivalent to 50 mg of sitagliptin and 779.86 mg of metformin equivalent to 1000 mg metformin HCl (JANUMET 50/1000).

Each film-coated tablet of JANUMET contains the following inactive ingredients: microcrystalline cellulose, polyvinylpyrrolidone, sodium lauryl sulfate, and sodium stearyl fumarate. In addition, the film coating contains the following inactive ingredients: polyvinyl alcohol, polyethylene glycol, talc, titanium dioxide, red iron oxide, and black iron oxide.

12 CLINICAL PHARMACOLOGY

12.1 Mechanism of Action

JANUMET

JANUMET combines two antihyperglycemic agents with complementary mechanisms of action to improve glycemic control in patients with type 2 diabetes mellitus: sitagliptin, a dipeptidyl peptidase-4 (DPP-4) inhibitor, and metformin HCl, a member of the biguanide class.

Sitagliptin

Sitagliptin is a DPP-4 inhibitor, which is believed to exert its actions in patients with type 2 diabetes by slowing the inactivation of incretin hormones. Concentrations of the active intact hormones are increased by sitagliptin, thereby increasing and prolonging the action of these hormones. Incretin hormones, including glucagon-like peptide-1 (GLP-1) and glucose-dependent insulinotropic polypeptide (GIP), are released by the intestine throughout the day, and levels are increased in response to a meal. These hormones are rapidly inactivated by the enzyme DPP-4. The incretins are part of an endogenous system involved in the physiologic regulation of glucose homeostasis. When blood glucose concentrations are normal or elevated, GLP-1 and GIP increase insulin synthesis and release from pancreatic beta cells by intracellular signaling pathways involving cyclic AMP. GLP-1 also lowers glucagon secretion from pancreatic alpha cells, leading to reduced hepatic glucose production. By increasing and prolonging active incretin levels, sitagliptin increases insulin release and decreases glucagon levels in the circulation in a glucose-dependent manner. Sitagliptin demonstrates selectivity for DPP-4 and does not inhibit DPP-8 or DPP-9 activity in vitro at concentrations approximating those from therapeutic doses.

Metformin

Metformin is an antihyperglycemic agent which improves glucose tolerance in patients with type 2 diabetes mellitus, lowering both basal and postprandial plasma glucose. Metformin decreases hepatic glucose production, decreases intestinal absorption of glucose, and improves insulin sensitivity by increasing peripheral glucose uptake and utilization. With metformin therapy, insulin secretion remains unchanged while fasting insulin levels and day-long plasma insulin response may decrease.

12.2 Pharmacodynamics

Sitagliptin

In patients with type 2 diabetes mellitus, administration of sitagliptin led to inhibition of DPP-4 enzyme activity for a 24-hour period. After an oral glucose load or a meal, this DPP-4 inhibition resulted in a 2- to 3-fold increase in circulating levels of active GLP-1 and GIP, decreased glucagon concentrations, and increased responsiveness of insulin release to glucose, resulting in higher C-peptide and insulin concentrations. The rise in insulin with the decrease in glucagon was associated with lower fasting glucose concentrations and reduced glucose excursion following an oral glucose load or a meal.

In studies with healthy subjects, sitagliptin did not lower blood glucose or cause hypoglycemia.

Sitagliptin and Metformin Coadministration

In a two-day study in healthy subjects, sitagliptin alone increased active GLP-1 concentrations, whereas metformin alone increased active and total GLP-1 concentrations to similar extents. Coadministration of sitagliptin and metformin had an additive effect on active GLP-1 concentrations. Sitagliptin, but not metformin, increased active GIP concentrations. It is unclear what these findings mean for changes in glycemic control in patients with type 2 diabetes mellitus.

Cardiac Electrophysiology

In a randomized, placebo-controlled crossover study, 79 healthy subjects were administered a single oral dose of sitagliptin 100 mg, sitagliptin 800 mg (8 times the recommended dose), and placebo. At the recommended dose of 100 mg, there was no effect on the QTc interval obtained at the peak plasma concentration, or at any other time during the study. Following the 800-mg dose, the maximum increase in the placebo-corrected mean change in QTc from baseline at 3 hours postdose was 8.0 msec. This increase is not considered to be clinically significant. At the 800-mg dose, peak sitagliptin plasma concentrations were approximately 11 times higher than the peak concentrations following a 100-mg dose.

In patients with type 2 diabetes mellitus administered sitagliptin 100 mg (N=81) or sitagliptin 200 mg (N=63) daily, there were no meaningful changes in QTc interval based on ECG data obtained at the time of expected peak plasma concentration.

12.3 Pharmacokinetics

Sitagliptin

The pharmacokinetics of sitagliptin have been extensively characterized in healthy subjects and patients with type 2 diabetes mellitus. Following a single oral 100-mg dose to healthy volunteers, mean plasma AUC of sitagliptin was 8.52 µM∙hr, Cmax was 950 nM, and apparent terminal half-life (t1/2) was 12.4 hours. Plasma AUC of sitagliptin increased in a dose-proportional manner and increased approximately 14% following 100 mg doses at steady-state compared to the first dose. The intra-subject and inter-subject coefficients of variation for sitagliptin AUC were small (5.8% and 15.1%). The pharmacokinetics of sitagliptin was generally similar in healthy subjects and in patients with type 2 diabetes mellitus.

Absorption

Sitagliptin

After oral administration of a 100 mg dose to healthy subjects, sitagliptin was rapidly absorbed with peak plasma concentrations (median Tmax) occurring 1 to 4 hours postdose. The absolute bioavailability of sitagliptin is approximately 87%.

Effect of Food

Coadministration of a high-fat meal with sitagliptin had no effect on the pharmacokinetics of sitagliptin.

Metformin

The absolute bioavailability of a metformin HCl 500-mg tablet given under fasting conditions is approximately 50-60%. Studies using single oral doses of metformin HCl tablets 500 mg to 1,500 mg, and 850 mg to 2,550 mg (approximately 1.3 times the maximum recommended daily dosage), indicate that there is a lack of dose proportionality with increasing doses, which is due to decreased absorption rather than an alteration in elimination.

Effect of Food

Food decreases the extent of and slightly delays the absorption of metformin, as shown by approximately a 40% lower mean peak plasma concentration (Cmax), a 25% lower area under the plasma concentration versus time curve (AUC), and a 35-minute prolongation of time to peak plasma concentration (Tmax) following administration of a single 850-mg tablet of metformin HCl with food, compared to the same tablet strength administered fasting. The clinical relevance of these decreases is unknown.

Distribution

Sitagliptin

The mean volume of distribution at steady state following a single 100-mg intravenous dose of sitagliptin to healthy subjects is approximately 198 liters. The fraction of sitagliptin reversibly bound to plasma proteins is low (38%).

Metformin

The apparent volume of distribution (V/F) of metformin following single oral doses of metformin HCl tablets 850 mg averaged 654 ± 358 L. Metformin is negligibly bound to plasma proteins, in contrast to sulfonylureas, which are more than 90% protein bound. Metformin partitions into erythrocytes, most likely as a function of time. At usual clinical doses and dosing schedules of metformin HCl tablets, steady-state plasma concentrations of metformin are reached within 24-48 hours and are generally <1 mcg/mL.

Elimination

Sitagliptin

Approximately 79% of sitagliptin is excreted unchanged in the urine with metabolism being a minor pathway of elimination. The apparent terminal t1/2 following a 100 mg oral dose of sitagliptin was approximately 12.4 hours and renal clearance was approximately 350 mL/min.

Metformin

Following oral administration, approximately 90% of the absorbed drug is eliminated via the renal route within the first 24 hours, with a plasma elimination half-life of approximately 6.2 hours. In blood, the elimination half-life is approximately 17.6 hours, suggesting that the erythrocyte mass may be a compartment of distribution.

Metabolism

Sitagliptin

Following a [^14C]sitagliptin oral dose, approximately 16% of the radioactivity was excreted as metabolites of sitagliptin. Six metabolites were detected at trace levels and are not expected to contribute to the plasma DPP-4 inhibitory activity of sitagliptin. In vitro studies indicated that the primary enzyme responsible for the limited metabolism of sitagliptin was CYP3A4, with contribution from CYP2C8.

Metformin

Intravenous single-dose studies in normal subjects demonstrate that metformin is excreted unchanged in the urine and does not undergo hepatic metabolism (no metabolites have been identified in humans) nor biliary excretion.

Excretion

Sitagliptin

Following administration of an oral [^14C]sitagliptin dose to healthy subjects, approximately 100% of the administered radioactivity was eliminated in feces (13%) or urine (87%) within one week of dosing.

Elimination of sitagliptin occurs primarily via renal excretion and involves active tubular secretion. Sitagliptin is a substrate for human organic anion transporter-3 (hOAT-3), which may be involved in the renal elimination of sitagliptin. The clinical relevance of hOAT-3 in sitagliptin transport has not been established. Sitagliptin is also a substrate of p-glycoprotein (P-gp), which may also be involved in mediating the renal elimination of sitagliptin. However, cyclosporine, a P-gp inhibitor, did not reduce the renal clearance of sitagliptin.

Metformin

Elimination of metformin occurs primarily via renal excretion. Renal clearance is approximately 3.5 times greater than creatinine clearance, which indicates that tubular secretion is the major route of metformin elimination.

Specific Populations

Patients with Renal Impairment

JANUMET

Studies characterizing the pharmacokinetics of sitagliptin and metformin after administration of JANUMET in renally impaired patients have not been performed [see Dosage and Administration (2.2)].

Sitagliptin

An approximately 2-fold increase in the plasma AUC of sitagliptin was observed in patients with moderate renal impairment with eGFR of 30 to less than 45 mL/min/1.73 m^2, and an approximately 4-fold increase was observed in patients with severe renal impairment including patients with end-stage renal disease (ESRD) on hemodialysis, as compared to normal healthy control subjects. [See Dosage and Administration (2.2).]

Metformin

In patients with decreased renal function, the plasma and blood half-life of metformin is prolonged and the renal clearance is decreased [see Contraindications (4); Warnings and Precautions (5.1)].

Patients with Hepatic Impairment

JANUMET

Studies characterizing the pharmacokinetics of sitagliptin and metformin after administration of JANUMET in patients with hepatic impairment have not been performed.

Sitagliptin

In patients with moderate hepatic impairment (Child-Pugh score 7 to 9), mean AUC and Cmax of sitagliptin increased approximately 21% and 13%, respectively, compared to healthy matched controls following administration of a single 100-mg dose of sitagliptin. These differences are not considered to be clinically meaningful. There is no clinical experience in patients with severe hepatic impairment (Child-Pugh score >9) [see Use in Specific Populations (8.7)].

Metformin

No pharmacokinetic studies of metformin have been conducted in patients with hepatic impairment.

Effects of Age, Body Mass Index (BMI), Gender, and Race

Sitagliptin

Based on a population pharmacokinetic analysis or a composite analysis of available pharmacokinetic data, BMI, gender, and race do not have a clinically meaningful effect on the pharmacokinetics of sitagliptin. When the effects of age on renal function are taken into account, age alone did not have a clinically meaningful impact on the pharmacokinetics of sitagliptin based on a population pharmacokinetic analysis. Elderly subjects (65 to 80 years) had approximately 19% higher plasma concentrations of sitagliptin compared to younger subjects.

Metformin

Limited data from controlled pharmacokinetic studies of metformin in healthy elderly subjects suggest that total plasma clearance of metformin is decreased, the half-life is prolonged, and Cmax is increased, compared to healthy young subjects. From these data, it appears that the change in metformin pharmacokinetics with aging is primarily accounted for by a change in renal function.

Metformin pharmacokinetic parameters did not differ significantly between normal subjects and patients with type 2 diabetes mellitus when analyzed according to gender. Similarly, in controlled clinical studies in patients with type 2 diabetes mellitus, the antihyperglycemic effect of metformin was comparable in males and females.

No studies of metformin pharmacokinetic parameters according to race have been performed. In controlled clinical studies of metformin in patients with type 2 diabetes mellitus, the antihyperglycemic effect was comparable in Whites (n=249), Blacks (n=51), and Hispanics (n=24).

Drug Interaction Studies

JANUMET

Coadministration of multiple doses of sitagliptin (50 mg) and metformin HCl (1000 mg) given twice daily did not meaningfully alter the pharmacokinetics of either sitagliptin or metformin in patients with type 2 diabetes.

Pharmacokinetic drug interaction studies with JANUMET have not been performed; however, such studies have been conducted with the individual components of JANUMET (sitagliptin and metformin HCl).

Sitagliptin

In Vitro Assessment of Drug Interactions

Sitagliptin is not an inhibitor of CYP isozymes CYP3A4, 2C8, 2C9, 2D6, 1A2, 2C19 or 2B6, and is not an inducer of CYP3A4. Sitagliptin is a P-gp substrate but does not inhibit P-gp mediated transport of digoxin. Based on these results, sitagliptin is considered unlikely to cause interactions with other drugs that utilize these pathways.

Sitagliptin is not extensively bound to plasma proteins. Therefore, the propensity of sitagliptin to be involved in clinically meaningful drug-drug interactions mediated by plasma protein binding displacement is very low.

In Vivo Assessment of Drug Interactions

Effects of Sitagliptin on Other Drugs

In clinical studies, sitagliptin did not meaningfully alter the pharmacokinetics of metformin, glyburide, simvastatin, rosiglitazone, digoxin, warfarin, or an oral contraception (ethinyl estradiol and norethindrone) (Table 5), providing in vivo evidence of a low propensity for causing drug interactions with substrates of CYP3A4, CYP2C8, CYP2C9, P-gp, and organic cationic transporter (OCT).

Table 5: Effect of Sitagliptin on Systemic Exposure of Coadministered Drugs
Coadministered Drug | Dose of Coadministered Drug [All doses administered as single dose unless otherwise specified.] | Dose of Sitagliptin | Geometric Mean Ratio (ratio with/without sitagliptin) No Effect = 1.00
 |  |  |  | AUC [AUC is reported as AUC0-∞ unless otherwise specified.] | Cmax
Digoxin | 0.25 mg [Multiple dose.] once daily for 10 days | 100 mg once daily for 10 days | Digoxin | 1.11 [AUC0-24hr.] | 1.18
Glyburide | 1.25 mg | 200 mg once daily for 6 days | Glyburide | 1.09 | 1.01
Simvastatin | 20 mg | 200 mg once daily for 5 days | Simvastatin | 0.85 [AUC0-last.] | 0.80
 |  | 200 mg once daily for 5 days | Simvastatin Acid | 1.12 | 1.06
Rosiglitazone | 4 mg | 200 mg once daily for 5 days | Rosiglitazone | 0.98 | 0.99
Warfarin | 30 mg single dose on day 5 | 200 mg once daily for 11 days | S(-) Warfarin | 0.95 | 0.89
 | 30 mg single dose on day 5 | 200 mg once daily for 11 days | R(+) Warfarin | 0.99 | 0.89
Ethinyl estradiol and norethindrone | 21 days once daily of 35 µg ethinyl estradiol with norethindrone 0.5 mg × 7 days, 0.75 mg × 7 days, 1.0 mg × 7 days | 200 mg once daily for 21 days | Ethinyl estradiol | 0.99 | 0.97
Ethinyl estradiol and norethindrone | 21 days once daily of 35 µg ethinyl estradiol with norethindrone 0.5 mg × 7 days, 0.75 mg × 7 days, 1.0 mg × 7 days | 200 mg once daily for 21 days | Norethindrone | 1.03 | 0.98
Metformin HCl | 1000 mg twice daily for 14 days | 50 mg twice daily for 7 days | Metformin | 1.02 [AUC0-12hr.] | 0.97

Effects of Other Drugs on Sitagliptin

Clinical data described below suggest that sitagliptin is not susceptible to clinically meaningful interactions by coadministered medications (Table 6).

Table 6: Effect of Coadministered Drugs on Systemic Exposure of Sitagliptin
Coadministered Drug | Dose of Coadministered Drug [All doses administered as single dose unless otherwise specified.] | Dose of Sitagliptin | Geometric Mean Ratio (ratio with/without coadministered drug) No Effect = 1.00
 |  |  |  | AUC [AUC is reported as AUC0-∞ unless otherwise specified.] | Cmax
Cyclosporine | 600 mg once daily | 100 mg once daily | Sitagliptin | 1.29 | 1.68
Metformin HCl | 1000 mg [Multiple dose.] twice daily for 14 days | 50 mg twice daily for 7 days | Sitagliptin | 1.02 [AUC0-12hr.] | 1.05

Metformin HCl

Table 7: Effect of Metformin HCl on Systemic Exposure of Coadministered Drugs
Coadministered Drug | Dose of Coadministered Drug [All doses administered as single dose unless otherwise specified.] | Dose of Metformin HCl | Geometric Mean Ratio (ratio with/without metformin) No Effect = 1.00
 |  |  |  | AUC [AUC is reported as AUC0-∞ unless otherwise specified.] | Cmax
Cimetidine | 400 mg | 850 mg | Cimetidine | 0.95 [AUC0-24hr.] | 1.01
Glyburide | 5 mg | 500 mg [GLUMETZA (metformin HCl extended-release tablets) 500 mg.] | Glyburide | 0.78 [Ratio of arithmetic means, p value of difference <0.05.] | 0.63
Furosemide | 40 mg | 850 mg | Furosemide | 0.87 | 0.69
Nifedipine | 10 mg | 850 mg | Nifedipine | 1.10 | 1.08
Propranolol | 40 mg | 850 mg | Propranolol | 1.01 | 0.94
Ibuprofen | 400 mg | 850 mg | Ibuprofen | 0.97 [Ratio of arithmetic means.] | 1.01

Table 8: Effect of Coadministered Drugs on Systemic Exposure of Metformin HCl
Coadministered Drug | Dose of Coadministered Drug [All doses administered as single dose unless otherwise specified.] | Dose of Metformin HCl | Geometric Mean Ratio (ratio with/without coadministered drug) No Effect = 1.00
 |  |  |  | AUC [AUC is reported as AUC0-∞ unless otherwise specified.] | Cmax
Glyburide | 5 mg | 500 mg [GLUMETZA (metformin HCl extended-release tablets) 500 mg.] | Metformin | 0.98 [Ratio of arithmetic means.] | 0.99
Furosemide | 40 mg | 850 mg | Metformin | 1.09 | 1.22
Nifedipine | 10 mg | 850 mg | Metformin | 1.16 | 1.21
Propranolol | 40 mg | 850 mg | Metformin | 0.90 | 0.94
Ibuprofen | 400 mg | 850 mg | Metformin | 1.05 | 1.07
Drugs that are eliminated by renal tubular secretion may increase the accumulation of metformin. [See Warnings and Precautions (5.1) and Drug Interactions (7).]
Cimetidine | 400 mg | 850 mg | Metformin | 1.40 | 1.61
Carbonic anhydrase inhibitors may cause metabolic acidosis. [See Warnings and Precautions (5.1) and Drug Interactions (7).]
Topiramate | 100 mg [Steady state 100 mg Topiramate every 12 hr + metformin HCl 500 mg every 12 hr AUC = AUC0-12hr.] | 500 mg | Metformin | 1.25 | 1.17

13 NONCLINICAL TOXICOLOGY

13.1 Carcinogenesis, Mutagenesis, Impairment of Fertility

JANUMET

No animal studies have been conducted with the combined products in JANUMET to evaluate carcinogenesis, mutagenesis or impairment of fertility. The following data are based on the findings in studies with sitagliptin and metformin individually.

Sitagliptin

A two-year carcinogenicity study was conducted in male and female rats given oral doses of sitagliptin of 50, 150, and 500 mg/kg/day. There was an increased incidence of combined liver adenoma/carcinoma in males and females and of liver carcinoma in females at 500 mg/kg. This dose results in exposures approximately 60 times the human exposure at the maximum recommended daily adult human dose (MRHD) of 100 mg/day based on AUC comparisons. Liver tumors were not observed at 150 mg/kg, approximately 20 times the human exposure at the MRHD. A two-year carcinogenicity study was conducted in male and female mice given oral doses of sitagliptin of 50, 125, 250, and 500 mg/kg/day. There was no increase in the incidence of tumors in any organ up to 500 mg/kg, approximately 70 times human exposure at the MRHD. Sitagliptin was not mutagenic or clastogenic with or without metabolic activation in the Ames bacterial mutagenicity assay, a Chinese hamster ovary (CHO) chromosome aberration assay, an in vitro cytogenetics assay in CHO, an in vitro rat hepatocyte DNA alkaline elution assay, and an in vivo micronucleus assay.

In rat fertility studies with oral gavage doses of 125, 250, and 1000 mg/kg, males were treated for 4 weeks prior to mating, during mating, up to scheduled termination (approximately 8 weeks total), and females were treated 2 weeks prior to mating through gestation day 7. No adverse effect on fertility was observed at 125 mg/kg (approximately 12 times human exposure at the MRHD of 100 mg/day based on AUC comparisons). At higher doses, nondose-related increased resorptions in females were observed (approximately 25 and 100 times human exposure at the MRHD based on AUC comparison).

Metformin

Long-term carcinogenicity studies have been performed in rats (dosing duration of 104 weeks) and mice (dosing duration of 91 weeks) at doses up to and including 900 mg/kg/day and 1500 mg/kg/day, respectively. These doses are both approximately four times the maximum recommended human daily dose of 2000 mg based on body surface area comparisons. No evidence of carcinogenicity with metformin was found in either male or female mice. Similarly, there was no tumorigenic potential observed with metformin in male rats. There was, however, an increased incidence of benign stromal uterine polyps in female rats treated with 900 mg/kg/day.

There was no evidence of a mutagenic potential of metformin in the following in vitro tests: Ames test (S. typhimurium), gene mutation test (mouse lymphoma cells), or chromosomal aberrations test (human lymphocytes). Results in the in vivo mouse micronucleus test were also negative. Fertility of male or female rats was unaffected by metformin when administered at doses as high as 600 mg/kg/day, which is approximately three times the maximum recommended human daily dose based on body surface area comparisons.

14 CLINICAL STUDIES

The coadministration of sitagliptin and metformin has been studied in patients with type 2 diabetes inadequately controlled on diet and exercise and in combination with other antihyperglycemic agents.

None of the clinical efficacy studies described below was conducted with JANUMET; however, bioequivalence of JANUMET with coadministered sitagliptin and metformin HCl tablets was demonstrated.

Sitagliptin and Metformin Coadministration in Patients with Type 2 Diabetes Inadequately Controlled on Diet and Exercise

A total of 1091 patients with type 2 diabetes and inadequate glycemic control on diet and exercise participated in a 24-week, randomized, double-blind, placebo-controlled factorial study designed to assess the efficacy of sitagliptin and metformin coadministration. Patients on an antihyperglycemic agent (N=541) underwent a diet, exercise, and drug washout period of up to 12 weeks duration. After the washout period, patients with inadequate glycemic control (A1C 7.5% to 11%) were randomized after completing a 2-week single-blind placebo run-in period. Patients not on antihyperglycemic agents at study entry (N=550) with inadequate glycemic control (A1C 7.5% to 11%) immediately entered the 2-week single-blind placebo run-in period and then were randomized. Approximately equal numbers of patients were randomized to receive placebo, 100 mg of sitagliptin once daily, 500 mg or 1000 mg of metformin HCl twice daily, or 50 mg of sitagliptin twice daily in combination with 500 mg or 1000 mg of metformin HCl twice daily. Patients who failed to meet specific glycemic goals during the study were treated with glyburide (glibenclamide) rescue.

Sitagliptin and metformin coadministration provided significant improvements in A1C, FPG, and 2-hour PPG compared to placebo, to metformin alone, and to sitagliptin alone (Table 9, Figure 1). Mean reductions from baseline in A1C were generally greater for patients with higher baseline A1C values. For patients not on an antihyperglycemic agent at study entry, mean reductions from baseline in A1C were: sitagliptin 100 mg once daily, -1.1%; metformin HCl 500 mg bid, -1.1%; metformin HCl 1000 mg bid, -1.2%; sitagliptin 50 mg bid with metformin HCl 500 mg bid, -1.6%; sitagliptin 50 mg bid with metformin HCl 1000 mg bid, -1.9%; and for patients receiving placebo, -0.2%. Lipid effects were generally neutral. The decrease in body weight in the groups given sitagliptin in combination with metformin was similar to that in the groups given metformin alone or placebo.

Table 9: Glycemic Parameters at Final Visit (24-Week Study) for Sitagliptin and Metformin, Alone and in Combination in Patients with Type 2 Diabetes Inadequately Controlled on Diet and Exercise [Intent-to-treat population using last observation on study prior to glyburide (glibenclamide) rescue therapy.]
 | Placebo | Sitagliptin 100 mg once daily | Metformin HCl 500 mg twice daily | Metformin HCl 1000 mg twice daily | Sitagliptin 50 mg twice daily + Metformin HCl 500 mg twice daily | Sitagliptin 50 mg twice daily + Metformin HCl 1000 mg twice daily
A1C (%) | N = 165 | N = 175 | N = 178 | N = 177 | N = 183 | N = 178
Baseline (mean) | 8.7 | 8.9 | 8.9 | 8.7 | 8.8 | 8.8
Change from baseline (adjusted mean [Least squares means adjusted for prior antihyperglycemic therapy status and baseline value.]) | 0.2 | -0.7 | -0.8 | -1.1 | -1.4 | -1.9
Difference from placebo (adjusted mean) (95% CI) |  | -0.8 [p<0.001 compared to placebo.] (-1.1, -0.6) | -1.0 (-1.2, -0.8) | -1.3 (-1.5, -1.1) | -1.6 (-1.8, -1.3) | -2.1 (-2.3, -1.8)
Patients (%) achieving A1C <7% | 15 (9%) | 35 (20%) | 41 (23%) | 68 (38%) | 79 (43%) | 118 (66%)
% Patients receiving rescue medication | 32 | 21 | 17 | 12 | 8 | 2
FPG (mg/dL) | N = 169 | N = 178 | N = 179 | N = 179 | N = 183 | N = 180
Baseline (mean) | 196 | 201 | 205 | 197 | 204 | 197
Change from baseline (adjusted mean) | 6 | -17 | -27 | -29 | -47 | -64
Difference from placebo (adjusted mean) (95% CI) |  | -23 (-33, -14) | -33 (-43, -24) | -35 (-45, -26) | -53 (-62, -43) | -70 (-79, -60)
2-hour PPG (mg/dL) | N = 129 | N = 136 | N = 141 | N = 138 | N = 147 | N = 152
Baseline (mean) | 277 | 285 | 293 | 283 | 292 | 287
Change from baseline (adjusted mean) | 0 | -52 | -53 | -78 | -93 | -117
Difference from placebo (adjusted mean) (95% CI) |  | -52 (-67, -37) | -54 (-69, -39) | -78 (-93, -63) | -93 (-107, -78) | -117 (-131, -102)

Figure 1: Mean Change from Baseline for A1C (%) over 24 Weeks with Sitagliptin and Metformin, Alone and in Combination in Patients with Type 2 Diabetes Inadequately Controlled with Diet and Exercise [All Patients Treated Population: least squares means adjusted for prior antihyperglycemic therapy and baseline value.]

Initial combination therapy or maintenance of combination therapy should be individualized and are left to the discretion of the health care provider.

Sitagliptin Add-on Therapy in Patients with Type 2 Diabetes Inadequately Controlled on Metformin Alone

A total of 701 patients with type 2 diabetes participated in a 24-week, randomized, double-blind, placebo-controlled study designed to assess the efficacy of sitagliptin in combination with metformin. Patients already on metformin (N=431) at a dose of at least 1500 mg per day were randomized after completing a 2-week, single-blind placebo run-in period. Patients on metformin and another antihyperglycemic agent (N=229) and patients not on any antihyperglycemic agents (off therapy for at least 8 weeks, N=41) were randomized after a run-in period of approximately 10 weeks on metformin HCl (at a dose of at least 1500 mg per day) in monotherapy. Patients were randomized to the addition of either 100 mg of sitagliptin or placebo, administered once daily. Patients who failed to meet specific glycemic goals during the studies were treated with pioglitazone rescue.

In combination with metformin, sitagliptin provided significant improvements in A1C, FPG, and 2-hour PPG compared to placebo with metformin (Table 10). Rescue glycemic therapy was used in 5% of patients treated with sitagliptin 100 mg and 14% of patients treated with placebo. A similar decrease in body weight was observed for both treatment groups.

Table 10: Glycemic Parameters at Final Visit (24-Week Study) of Sitagliptin as Add-on Combination Therapy with Metformin [Intent-to-treat population using last observation on study prior to pioglitazone rescue therapy.]
 | Sitagliptin 100 mg once daily + Metformin | Placebo + Metformin
A1C (%) | N = 453 | N = 224
Baseline (mean) | 8.0 | 8.0
Change from baseline (adjusted mean [Least squares means adjusted for prior antihyperglycemic therapy and baseline value.]) | -0.7 | -0.0
Difference from placebo + metformin (adjusted mean) (95% CI) | -0.7 [p<0.001 compared to placebo + metformin.] (-0.8, -0.5)
Patients (%) achieving A1C <7% | 213 (47%) | 41 (18%)
FPG (mg/dL) | N = 454 | N = 226
Baseline (mean) | 170 | 174
Change from baseline (adjusted mean) | -17 | 9
Difference from placebo + metformin (adjusted mean) (95% CI) | -25 (-31, -20)
2-hour PPG (mg/dL) | N = 387 | N = 182
Baseline (mean) | 275 | 272
Change from baseline (adjusted mean) | -62 | -11
Difference from placebo + metformin (adjusted mean) (95% CI) | -51 (-61, -41)

Sitagliptin Add-on Therapy in Patients with Type 2 Diabetes Inadequately Controlled on the Combination of Metformin and Glimepiride

A total of 441 patients with type 2 diabetes participated in a 24-week, randomized, double-blind, placebo-controlled study designed to assess the efficacy of sitagliptin in combination with glimepiride, with or without metformin. Patients entered a run-in treatment period on glimepiride (≥4 mg per day) alone or glimepiride in combination with metformin HCl (≥1500 mg per day). After a dose-titration and dose-stable run-in period of up to 16 weeks and a 2-week placebo run-in period, patients with inadequate glycemic control (A1C 7.5% to 10.5%) were randomized to the addition of either 100 mg of sitagliptin or placebo, administered once daily. Patients who failed to meet specific glycemic goals during the studies were treated with pioglitazone rescue.

Patients receiving sitagliptin with metformin and glimepiride had significant improvements in A1C and FPG compared to patients receiving placebo with metformin and glimepiride (Table 11), with mean reductions from baseline relative to placebo in A1C of -0.9% and in FPG of -21 mg/dL. Rescue therapy was used in 8% of patients treated with add-on sitagliptin 100 mg and 29% of patients treated with add-on placebo. The patients treated with add-on sitagliptin had a mean increase in body weight of 1.1 kg vs. add-on placebo (+0.4 kg vs. -0.7 kg). In addition, add-on sitagliptin resulted in an increased rate of hypoglycemia compared to add-on placebo. [See Warnings and Precautions (5.6); Adverse Reactions (6.1).]

Table 11: Glycemic Parameters at Final Visit (24-Week Study) for Sitagliptin in Combination with Metformin and Glimepiride [Intent-to-treat population using last observation on study prior to pioglitazone rescue therapy.]
 | Sitagliptin 100 mg + Metformin and Glimepiride | Placebo + Metformin and Glimepiride
A1C (%) | N = 115 | N = 105
Baseline (mean) | 8.3 | 8.3
Change from baseline (adjusted mean [Least squares means adjusted for prior antihyperglycemic therapy status and baseline value.]) | -0.6 | 0.3
Difference from placebo (adjusted mean) (95% CI) | -0.9 [p<0.001 compared to placebo.] (-1.1, -0.7)
Patients (%) achieving A1C <7% | 26 (23%) | 1 (1%)
FPG (mg/dL) | N = 115 | N = 109
Baseline (mean) | 179 | 179
Change from baseline (adjusted mean) | -8 | 13
Difference from placebo (adjusted mean) (95% CI) | -21 (-32, -10)

Sitagliptin Add-on Therapy in Patients with Type 2 Diabetes Inadequately Controlled on the Combination of Metformin and Rosiglitazone

A total of 278 patients with type 2 diabetes participated in a 54-week, randomized, double-blind, placebo-controlled study designed to assess the efficacy of sitagliptin in combination with metformin and rosiglitazone. Patients on dual therapy with metformin HCl ≥1500 mg/day and rosiglitazone ≥4 mg/day or with metformin HCl ≥1500 mg/day and pioglitazone ≥30 mg/day (switched to rosiglitazone ≥4 mg/day) entered a dose-stable run-in period of 6 weeks. Patients on other dual therapy were switched to metformin HCl ≥1500 mg/day and rosiglitazone ≥4 mg/day in a dose titration/stabilization run-in period of up to 20 weeks in duration. After the run-in period, patients with inadequate glycemic control (A1C 7.5% to 11%) were randomized 2:1 to the addition of either 100 mg of sitagliptin or placebo, administered once daily. Patients who failed to meet specific glycemic goals during the studies were treated with glipizide (or other sulfonylurea) rescue. The primary time point for evaluation of glycemic parameters was Week 18.

In combination with metformin and rosiglitazone, sitagliptin provided significant improvements in A1C, FPG, and 2-hour PPG compared to placebo with metformin and rosiglitazone (Table 12) at Week 18. At Week 54, mean reduction in A1C was -1.0% for patients treated with sitagliptin and -0.3% for patients treated with placebo in an analysis based on the intent-to-treat population. Rescue therapy was used in 18% of patients treated with sitagliptin 100 mg and 40% of patients treated with placebo. There was no significant difference between sitagliptin and placebo in body weight change.

Table 12: Glycemic Parameters at Week 18 for Sitagliptin in Add-on Combination Therapy with Metformin and Rosiglitazone [Intent-to-treat population using last observation on study prior to glipizide (or other sulfonylurea) rescue therapy.]
 | Week 18
 | Sitagliptin 100 mg + Metformin + Rosiglitazone | Placebo + Metformin + Rosiglitazone
A1C (%) | N = 176 | N = 93
Baseline (mean) | 8.8 | 8.7
Change from baseline (adjusted mean [Least squares means adjusted for prior antihyperglycemic therapy status and baseline value.]) | -1.0 | -0.4
Difference from placebo + rosiglitazone + metformin (adjusted mean) (95% CI) | -0.7 [p<0.001 compared to placebo + metformin + rosiglitazone.] (-0.9,-0.4)
Patients (%) achieving A1C <7% | 39 (22%) | 9 (10%)
FPG (mg/dL) | N = 179 | N = 94
Baseline (mean) | 181 | 182
Change from baseline (adjusted mean) | -30 | -11
Difference from placebo + rosiglitazone + metformin (adjusted mean) (95% CI) | -18 (-26, -10)
2-hour PPG (mg/dL) | N = 152 | N = 80
Baseline (mean) | 256 | 248
Change from baseline (adjusted mean) | -59 | -21
Difference from placebo + rosiglitazone + metformin (adjusted mean) (95% CI) | -39 (-51, -26)

Sitagliptin Add-on Therapy in Patients with Type 2 Diabetes Inadequately Controlled on the Combination of Metformin and Insulin

A total of 641 patients with type 2 diabetes participated in a 24-week, randomized, double-blind, placebo-controlled study designed to assess the efficacy of sitagliptin as add-on to insulin therapy. Approximately 75% of patients were also taking metformin. Patients entered a 2-week, single-blind run-in treatment period on pre-mixed, long-acting, or intermediate-acting insulin, with or without metformin HCl (≥1500 mg per day). Patients using short-acting insulins were excluded unless the short-acting insulin was administered as part of a pre-mixed insulin. After the run-in period, patients with inadequate glycemic control (A1C 7.5% to 11%) were randomized to the addition of either 100 mg of sitagliptin (N=229) or placebo (N=233), administered once daily. Patients were on a stable dose of insulin prior to enrollment with no changes in insulin dose permitted during the run-in period. Patients who failed to meet specific glycemic goals during the double-blind treatment period were to have uptitration of the background insulin dose as rescue therapy.

Among patients also receiving metformin, the median daily insulin (pre-mixed, intermediate or long acting) dose at baseline was 40 units in the sitagliptin-treated patients and 42 units in the placebo-treated patients. The median change from baseline in daily dose of insulin was zero for both groups at the end of the study. Patients receiving sitagliptin with metformin and insulin had significant improvements in A1C, FPG and 2-hour PPG compared to patients receiving placebo with metformin and insulin (Table 13). The adjusted mean change from baseline in body weight was -0.3 kg in patients receiving sitagliptin with metformin and insulin and -0.2 kg in patients receiving placebo with metformin and insulin. There was an increased rate of hypoglycemia in patients treated with sitagliptin. [See Warnings and Precautions (5.6); Adverse Reactions (6.1).]

Table 13: Glycemic Parameters at Final Visit (24-Week Study) for Sitagliptin as Add-on Combination Therapy with Metformin and Insulin [Intent-to-treat population using last observation on study prior to rescue therapy.]
 | Sitagliptin 100 mg + Metformin + Insulin | Placebo + Metformin + Insulin
A1C (%) | N = 223 | N = 229
Baseline (mean) | 8.7 | 8.6
Change from baseline (adjusted mean [Least squares means adjusted for insulin use at the screening visit, type of insulin used at the screening visit (pre-mixed vs. non pre-mixed [intermediate- or long-acting]), and baseline value.] , [Treatment by insulin stratum interaction was not significant (p >0.10).]) | -0.7 | -0.1
Difference from placebo (adjusted mean) (95% CI) | -0.5 [p<0.001 compared to placebo.] (-0.7, -0.4)
Patients (%) achieving A1C <7% | 32 (14%) | 12 (5%)
FPG (mg/dL) | N = 225 | N = 229
Baseline (mean) | 173 | 176
Change from baseline (adjusted mean) | -22 | -4
Difference from placebo (adjusted mean) (95% CI) | -18 (-28, -8.4)
2-hour PPG (mg/dL) | N = 182 | N = 189
Baseline (mean) | 281 | 281
Change from baseline (adjusted mean) | -39 | 1
Difference from placebo (adjusted mean) (95% CI) | -40 (-53, -28)

Maintenance of Sitagliptin During Initiation and Titration of Insulin Glargine

A total of 746 patients with type 2 diabetes (mean baseline HbA1C 8.8%, disease duration 10.8 years) participated in a 30-week, randomized, double-blind, placebo-controlled study to assess the efficacy and safety of continuing sitagliptin during the initiation and uptitration of insulin glargine. Patients who were on a stable dose of metformin HCl (≥1500 mg/day) in combination with a DPP-4 inhibitor and/or sulfonylurea but with inadequate glycemic control (A1C 7.5% to 11%) were enrolled in the study. Those on metformin and sitagliptin (100 mg/day) directly entered the double-blind treatment period; those on another DPP-4 inhibitor and/or on a sulfonylurea entered a 4-8 week run-in period in which they were maintained on metformin and switched to sitagliptin (100 mg); other DPP-4 inhibitors and sulfonylureas were discontinued. At randomization patients were randomized either to continue sitagliptin or to discontinue sitagliptin and switch to a matching placebo. On the day of randomization, insulin glargine was initiated at a dose of 10 units subcutaneously in the evening. Patients were instructed to uptitrate their insulin dose in the evening based on fasting blood glucose measurements to achieve a target of 72-100 mg/dL.

At 30 weeks, the mean reduction in A1C was greater in the sitagliptin group than in the placebo group (Table 14). At the end of the trial, 27.3% of patients in the sitagliptin group and 27.3% in the placebo group had a fasting plasma glucose (FPG) in the target range; there was no significant difference in insulin dose between arms.

Table 14: Change from Baseline in A1C and FPG at Week 30 in the Maintenance of Sitagliptin During Initiation and Titration of Insulin Glargine Study
 | Sitagliptin 100 mg +Metformin + Insulin Glargine | Placebo +Metformin + Insulin Glargine
A1C (%) | N = 373 [N is the number of randomized and treated patients.] | N = 370
Baseline (mean) | 8.8 | 8.8
Week 30 (mean) | 6.9 | 7.3
Change from baseline (adjusted mean) [Analysis of Covariance including all post-baseline data regardless of rescue or treatment discontinuation. Model estimates calculated using multiple imputation to model washout of the treatment effect using placebo data for all subjects having missing Week 30 data.] | -1.9 | -1.4
Difference from placebo (adjusted mean) (95% CI) | -0.4 (-0.6, -0.3) [p<0.001 compared to placebo.]
Patients (%) with A1C <7% | 202 (54.2%) | 131 (35.4%)
FPG (mg/dL) | N = 373 | N = 370
Baseline (mean) | 199 | 201
Week 30 (mean) | 118 | 123
Change from baseline (adjusted mean) | -81 | -76

Sitagliptin Add-on Therapy vs. Glipizide Add-on Therapy in Patients with Type 2 Diabetes Inadequately Controlled on Metformin

The efficacy of sitagliptin was evaluated in a 52-week, double-blind, glipizide-controlled noninferiority trial in patients with type 2 diabetes. Patients not on treatment or on other antihyperglycemic agents entered a run-in treatment period of up to 12 weeks duration with metformin monotherapy (dose of ≥1500 mg per day) which included washout of medications other than metformin, if applicable. After the run-in period, those with inadequate glycemic control (A1C 6.5% to 10%) were randomized 1:1 to the addition of sitagliptin 100 mg once daily or glipizide for 52 weeks. Patients receiving glipizide were given an initial dosage of 5 mg/day and then electively titrated over the next 18 weeks to a maximum dosage of 20 mg/day as needed to optimize glycemic control. Thereafter, the glipizide dose was to be kept constant, except for down-titration to prevent hypoglycemia. The mean dose of glipizide after the titration period was 10 mg.

After 52 weeks, sitagliptin and glipizide had similar mean reductions from baseline in A1C in the intent-to-treat analysis (Table 15). These results were consistent with the per protocol analysis (Figure 2). A conclusion in favor of the non-inferiority of sitagliptin to glipizide may be limited to patients with baseline A1C comparable to those included in the study (over 70% of patients had baseline A1C less than 8% and over 90% had A1C less than 9%).

Table 15: Glycemic Parameters in a 52-Week Study Comparing Sitagliptin to Glipizide as Add-On Therapy in Patients Inadequately Controlled on Metformin (Intent-to-Treat Population) [The intent-to-treat analysis used the patients' last observation in the study prior to discontinuation.]
 | Sitagliptin 100 mg + Metformin | Glipizide + Metformin
A1C (%) | N = 576 | N = 559
Baseline (mean) | 7.7 | 7.6
Change from baseline (adjusted mean [Least squares means adjusted for prior antihyperglycemic therapy status and baseline A1C value.]) | -0.5 | -0.6
FPG (mg/dL) | N = 583 | N = 568
Baseline (mean) | 166 | 164
Change from baseline (adjusted mean) | -8 | -8

Figure 2: Mean Change from Baseline for A1C (%) Over 52 Weeks in a Study Comparing Sitagliptin to Glipizide as Add-On Therapy in Patients Inadequately Controlled on Metformin (Per Protocol Population) [The per protocol population (mean baseline A1C of 7.5%) included patients without major protocol violations who had observations at baseline and at Week 52.]

The incidence of hypoglycemia in the sitagliptin group (4.9%) was significantly (p<0.001) lower than that in the glipizide group (32.0%). Patients treated with sitagliptin exhibited a significant mean decrease from baseline in body weight compared to a significant weight gain in patients administered glipizide (-1.5 kg vs. +1.1 kg).

16 HOW SUPPLIED/STORAGE AND HANDLING

Tablets supplied as follows:

Contents | Description | How Supplied | NDC
50 mg sitagliptin and 500 mg metformin HCl | light pink, capsule-shaped, film-coated tablets with “575” debossed on one side | unit-of-use bottles of 60 | NDC 0006-0575-61
50 mg sitagliptin and 500 mg metformin HCl | light pink, capsule-shaped, film-coated tablets with “575” debossed on one side | unit-of-use bottles of 180 | NDC 0006-0575-62
50 mg sitagliptin and 500 mg metformin HCl | light pink, capsule-shaped, film-coated tablets with “575” debossed on one side | bulk bottles of 1000 | NDC 0006-0575-82
50 mg sitagliptin and 1000 mg metformin HCl | red, capsule-shaped, film-coated tablets with “577” debossed on one side | unit-of-use bottles of 60 | NDC 0006-0577-61
50 mg sitagliptin and 1000 mg metformin HCl | red, capsule-shaped, film-coated tablets with “577” debossed on one side | unit-of-use bottles of 180 | NDC 0006-0577-62
50 mg sitagliptin and 1000 mg metformin HCl | red, capsule-shaped, film-coated tablets with “577” debossed on one side | bulk bottles of 1000 | NDC 0006-0577-82

STORAGE AND HANDLING

Store at 20-25°C (68-77°F), excursions permitted to 15-30°C (59-86°F). [See USP Controlled Room Temperature.]

17 PATIENT COUNSELING INFORMATION

Advise the patient to read the FDA-approved patient labeling (Medication Guide).

Lactic Acidosis

Explain the risks of lactic acidosis, its symptoms, and conditions that predispose to its development. Advise patients to discontinue JANUMET immediately and to promptly notify their healthcare provider if unexplained hyperventilation, myalgias, malaise, unusual somnolence or other nonspecific symptoms occur. Counsel patients against excessive alcohol intake and inform patients about the importance of regular testing of renal function while receiving JANUMET. Instruct patients to inform their doctor that they are taking JANUMET prior to any surgical or radiological procedure, as temporary discontinuation may be required [see Warnings and Precautions (5.1)].

Pancreatitis

Inform patients that acute pancreatitis has been reported during postmarketing use of JANUMET. Inform patients that persistent severe abdominal pain, sometimes radiating to the back, which may or may not be accompanied by vomiting, is the hallmark symptom of acute pancreatitis. Instruct patients to promptly discontinue JANUMET and contact their physician if persistent severe abdominal pain occurs [see Warnings and Precautions (5.2)].

Heart Failure

Inform patients of the signs and symptoms of heart failure. Before initiating JANUMET, ask patients about a history of heart failure or other risk factors for heart failure including moderate to severe renal impairment. Instruct patients to contact their health care provider as soon as possible if they experience symptoms of heart failure, including increasing shortness of breath, rapid increase in weight or swelling of the feet [see Warnings and Precautions (5.3)].

Vitamin B12 Deficiency

Inform patients about the importance of regular monitoring of hematological parameters while receiving JANUMET [see Warnings and Precautions (5.5)].

Hypoglycemia

Inform patients that the incidence of hypoglycemia is increased when JANUMET is added to an insulin secretagogue (e.g., sulfonylurea) or insulin therapy. Explain to patients receiving JANUMET in combination with these medications the risks of hypoglycemia, its symptoms and treatment, and conditions that predispose to its development [see Warnings and Precautions (5.6)].

Hypersensitivity Reactions

Inform patients that allergic reactions have been reported during postmarketing use of sitagliptin, one of the components of JANUMET. If symptoms of allergic reactions (including rash, hives, and swelling of the face, lips, tongue, and throat that may cause difficulty in breathing or swallowing) occur, patients must stop taking JANUMET and seek medical advice promptly.

Severe and Disabling Arthralgia

Inform patients that severe and disabling joint pain may occur with this class of drugs. The time to onset of symptoms can range from one day to years. Instruct patients to seek medical advice if severe joint pain occurs [see Warnings and Precautions (5.8)].

Bullous Pemphigoid

Inform patients that bullous pemphigoid may occur with this class of drugs. Instruct patients to seek medical advice if blisters or erosions occur [see Warnings and Precautions (5.9)].

Females of Reproductive Age:

Inform females that treatment with JANUMET may result in ovulation in some premenopausal anovulatory women which may lead to unintended pregnancy [see Use in Specific Populations (8.3)].

Administration Instructions

Inform patients that the tablets must never be split or divided before swallowing.

Dist. by: Merck Sharp & Dohme LLC
Rahway, NJ 07065, USA

For patent information: www.msd.com/research/patent

The trademarks depicted herein are owned by their respective companies.

Copyright © 2007-2022 Merck & Co., Inc., Rahway, NJ, USA, and its affiliates.
All rights reserved.

uspi-mk0431a-t-2207r024

Medication Guide
JANUMET® (JAN-you-met)
(sitagliptin and metformin hydrochloride)
tablets, for oral use

Read this Medication Guide carefully before you start taking JANUMET and each time you get a refill. There may be new information. This information does not take the place of talking with your doctor about your medical condition or your treatment. If you have any questions about JANUMET, ask your doctor or pharmacist.

What is the most important information I should know about JANUMET?

JANUMET can cause serious side effects, including:

1. Lactic Acidosis. Metformin, one of the medicines in JANUMET, can cause a rare but serious condition called lactic acidosis (a buildup of an acid in the blood) that can cause death. Lactic acidosis is a medical emergency and must be treated in the hospital.

Stop taking JANUMET and call your doctor right away if you have any of the following symptoms, which could be signs of lactic acidosis:

- you feel cold in your hands or feet
- you feel dizzy or lightheaded
- you have a slow or irregular heartbeat
- you feel very weak or tired
- you have unusual (not normal) muscle pain
- you have trouble breathing
- you feel sleepy or drowsy
- you have stomach pains, nausea or vomiting

Most people who have had lactic acidosis with metformin have other things that, combined with the metformin, led to the lactic acidosis. Tell your doctor if you have any of the following, because you have a higher chance for getting lactic acidosis with JANUMET if you:

- have severe kidney problems or your kidneys are affected by certain x-ray tests that use injectable dye
- have liver problems
- drink alcohol very often, or drink a lot of alcohol in short-term "binge" drinking
- get dehydrated (lose a large amount of body fluids). This can happen if you are sick with a fever, vomiting, or diarrhea. Dehydration can also happen when you sweat a lot with activity or exercise and do not drink enough fluids.
- have surgery
- have a heart attack, severe infection, or stroke
- are 65 years of age or older

The best way to keep from having a problem with lactic acidosis from metformin is to tell your doctor if you have any of the problems in the list above. Your doctor may decide to stop your JANUMET for a while if you have any of these things.

JANUMET can have other serious side effects. See "What are the possible side effects of JANUMET?"

2. Pancreatitis (inflammation of the pancreas) which may be severe and lead to death. Certain medical problems make you more likely to get pancreatitis.

Before you start taking JANUMET, tell your doctor if you have ever had:

- pancreatitis
- stones in your gallbladder (gallstones)
- a history of alcoholism
- high blood triglyceride levels

Stop taking JANUMET and call your doctor right away if you have pain in your stomach area (abdomen) that is severe and will not go away. The pain may be felt going from your abdomen through to your back. The pain may happen with or without vomiting. These may be symptoms of pancreatitis.

3. Heart failure. Heart failure means that your heart does not pump blood well enough.

Before you start taking JANUMET, tell your doctor if you have ever had heart failure or have problems with your kidneys.
Contact your doctor right away if you have any of the following symptoms:

- increasing shortness of breath or trouble breathing, especially when you lie down
- swelling or fluid retention, especially in the feet, ankles or legs
- an unusually fast increase in weight
- unusual tiredness

These may be symptoms of heart failure.

What is JANUMET?

- JANUMET is a prescription medicine that contains 2 prescription diabetes medicines, sitagliptin (JANUVIA) and metformin. JANUMET can be used along with diet and exercise to lower blood sugar in adults with type 2 diabetes.
- JANUMET is not for people with type 1 diabetes.
- If you have had pancreatitis (inflammation of the pancreas) in the past, it is not known if you have a higher chance of getting pancreatitis while you take JANUMET.
- The safety and effectiveness of JANUMET have not been established in pediatric patients.

Who should not take JANUMET?

Do not take JANUMET if you:

- have severe kidney problems.
- have diabetic ketoacidosis.
- are allergic to any of the ingredients in JANUMET. See the end of this Medication Guide for a complete list of ingredients in JANUMET.

Symptoms of a serious allergic reaction to JANUMET may include rash, raised red patches on your skin (hives) or swelling of the face, lips, tongue, and throat that may cause difficulty in breathing or swallowing.

What should I tell my doctor before taking JANUMET?

Before you take JANUMET, tell your doctor about all of your medical conditions, including if you:

- have or have had inflammation of your pancreas (pancreatitis).
- have kidney problems.
- have liver problems.
- have heart failure.
- drink alcohol very often or drink a lot of alcohol in short-term "binge" drinking.
- are going to get an injection of dye or contrast agents for an x-ray procedure. JANUMET may need to be stopped for a short time. Talk to your doctor about when you should stop JANUMET and when you should start JANUMET again. See "What is the most important information I should know about JANUMET?".
- have low levels of vitamin B12 in your blood.
- are pregnant or plan to become pregnant. It is not known if JANUMET will harm your unborn baby. If you are pregnant, talk with your doctor about the best way to control your blood sugar while you are pregnant.
- are breastfeeding or plan to breastfeed. It is not known if JANUMET will pass into your breast milk. Talk with your doctor about the best way to feed your baby if you are taking JANUMET.
- are a woman who has not gone through menopause (premenopausal) who does not have periods regularly or at all. JANUMET can cause the release of an egg from an ovary in a woman (ovulation). This can increase your chance of getting pregnant. Tell your doctor right away if you become pregnant while taking JANUMET.

Tell your doctor about all the medicines you take, including prescription and over-the-counter medicines, vitamins, and herbal supplements. JANUMET may affect the way other medicines work and other medicines may affect how JANUMET works.

Know the medicines you take. Keep a list of your medicines and show it to your doctor and pharmacist when you get a new medicine.

How should I take JANUMET?

- Take JANUMET exactly as your doctor tells you. Your doctor will tell you how many JANUMET tablets to take and when you should take them.
- Your doctor may change your dose of JANUMET if needed.
- Your doctor may tell you to take JANUMET along with certain other diabetes medicines. Low blood sugar (hypoglycemia) can happen more often when JANUMET is taken with certain other diabetes medicines. See "What are the possible side effects of JANUMET?".
- Take JANUMET with meals to help to lower your chance of having an upset stomach.
- Do not break or cut JANUMET tablets before swallowing. If you cannot swallow JANUMET tablets whole, tell your doctor.
- Continue to take JANUMET as long as your doctor tells you.
- If you take too much JANUMET, call your doctor or local Poison Control Center right away.
- If you miss a dose, take it as soon as you remember. If you do not remember until it is time for your next dose, skip the missed dose and go back to your regular schedule. Do not take 2 doses of JANUMET at the same time.
- You may need to stop taking JANUMET for a short time. Call your doctor for instructions if you:
  - are dehydrated (have lost too much body fluid). Dehydration can occur if you are sick with severe vomiting, diarrhea or fever, or if you drink a lot less fluid than normal.
  - plan to have surgery.
  - are going to get an injection of dye or contrast agent for an x-ray procedure. See "What is the most important information I should know about JANUMET?" and "What should I tell my doctor before taking JANUMET?".
- When your body is under some types of stress, such as fever, trauma (such as a car accident), infection or surgery, the amount of diabetes medicine that you need may change. Tell your doctor right away if you have any of these problems and follow your doctor's instructions.
- Check your blood sugar as your doctor tells you to.
- Stay on your prescribed diet and exercise program while taking JANUMET.
- Talk to your doctor about how to prevent, recognize and manage low blood sugar (hypoglycemia), high blood sugar (hyperglycemia), and problems you have because of your diabetes.
- Your doctor will check your diabetes with regular blood tests, including your blood sugar levels and your hemoglobin A1C.
- Your doctor will do blood tests to check how well your kidneys are working before and during your treatment with JANUMET.

What are the possible side effects of JANUMET?

JANUMET may cause serious side effects, including:

- See "What is the most important information I should know about JANUMET?".
- Kidney problems, sometimes requiring dialysis.
- Low vitamin B12 (vitamin B12 deficiency). Using metformin for long periods of time may cause a decrease in the amount of vitamin B12 in your blood, especially if you have had low vitamin B12 blood levels before. Your doctor may do blood tests to check your vitamin B12 levels.
- Low blood sugar (hypoglycemia). If you take JANUMET with another medicine that can cause low blood sugar, such as a sulfonylurea or insulin, your risk of getting low blood sugar is higher. The dose of your sulfonylurea medicine or insulin may need to be lowered while you use JANUMET. Signs and symptoms of low blood sugar may include:

- headache
- drowsiness

- irritability
- hunger

- dizziness
- confusion

- sweating
- feeling jittery

- weakness
- fast heart beat

- Serious allergic reactions. If you have any symptoms of a serious allergic reaction, stop taking JANUMET and call your doctor right away or get emergency medical help. See "Who should not take JANUMET?". Your doctor may give you a medicine for your allergic reaction and prescribe a different medicine for your diabetes.
- Joint pain. Some people who take medicines called DPP-4 inhibitors, one of the medicines in JANUMET, may develop joint pain that can be severe. Call your doctor if you have severe joint pain.
- Skin reaction. Some people who take medicines called DPP-4 inhibitors, one of the medicines in JANUMET, may develop a skin reaction called bullous pemphigoid that can require treatment in a hospital. Tell your doctor right away if you develop blisters or the breakdown of the outer layer of your skin (erosion). Your doctor may tell you to stop taking JANUMET.

The most common side effects of JANUMET include:

- stuffy or runny nose and sore throat
- gas, upset stomach, indigestion
- headache

- upper respiratory infection
- weakness
- diarrhea

- low blood sugar (hypoglycemia) when used in combination with certain medicines, such as a sulfonylurea or insulin
- nausea and vomiting

Taking JANUMET with meals can help lessen the common stomach side effects of metformin that usually happen at the beginning of treatment. If you have unusual or sudden stomach problems, talk with your doctor. Stomach problems that start later during treatment may be a sign of something more serious.

JANUMET may have other side effects, including swelling of the hands or legs. Swelling of the hands and legs can happen if you take JANUMET in combination with rosiglitazone (Avandia). Rosiglitazone is another type of diabetes medicine.

Tell your doctor if you have any side effect that bothers you, or does not go away.

These are not all the possible side effects of JANUMET. For more information, ask your doctor or pharmacist.

Call your doctor for medical advice about side effects. You may report side effects to FDA at 1-800-FDA-1088.

How should I store JANUMET?

Store JANUMET at room temperature, between 68°F to 77°F (20°C to 25°C).

Keep JANUMET and all medicines out of the reach of children.

General information about the safe and effective use of JANUMET.

Medicines are sometimes prescribed for purposes other than those listed in a Medication Guide. Do not use JANUMET for a condition for which it was not prescribed. Do not give JANUMET to other people, even if they have the same symptoms you have. It may harm them.

This Medication Guide summarizes the most important information about JANUMET. If you would like to know more information, talk with your doctor. You can ask your doctor or pharmacist for information about JANUMET that is written for health professionals.

What are the ingredients in JANUMET?

Active ingredients: sitagliptin and metformin hydrochloride

Inactive ingredients: microcrystalline cellulose, polyvinylpyrrolidone, sodium lauryl sulfate, and sodium stearyl fumarate. The tablet film coating contains the following inactive ingredients: polyvinyl alcohol, polyethylene glycol, talc, titanium dioxide, red iron oxide, and black iron oxide.

Dist. by: Merck Sharp & Dohme LLC
Rahway, NJ 07065, USA
For more information go to www.janumet.com or call 1-800-622-4477.
For patent information: www.msd.com/research/patent .
The trademarks depicted herein are owned by their respective companies.
Copyright © 2010-2022 Merck & Co., Inc., Rahway, NJ, USA, and its affiliates.
All rights reserved.
usmg-mk0431a-t-2207r015

This Medication Guide has been approved by the U.S. Food and Drug Administration.

Revised: 07/2022

PRINCIPAL DISPLAY PANEL - 50 mg/500 mg Tablet Bottle Label

NDC 0006-0575-61

Janumet®
(sitagliptin and
metformin HCl) tablets

50 mg/500 mg

Dispense the accompanying Medication
Guide to each patient.

Each tablet contains 64.25 mg sitagliptin phosphate
(equivalent to 50 mg sitagliptin) and 500 mg
metformin hydrochloride.

Rx only

60 Tablets

PRINCIPAL DISPLAY PANEL - 50 mg/1,000 mg Tablet Bottle Label

NDC 0006-0577-61

Janumet®
(sitagliptin and
metformin HCl) tablets

50 mg/1,000 mg

Dispense the accompanying Medication Guide
to each patient.

Each tablet contains 64.25 mg sitagliptin phosphate
(equivalent to 50 mg sitagliptin) and 1,000 mg
metformin hydrochloride.

Rx only

60 Tablets